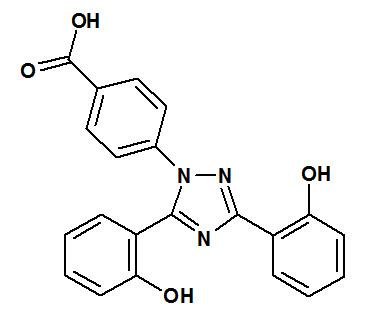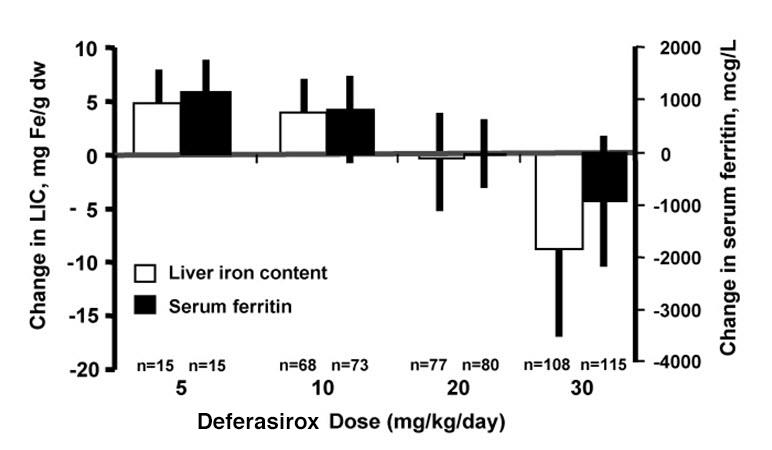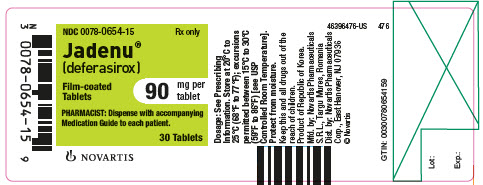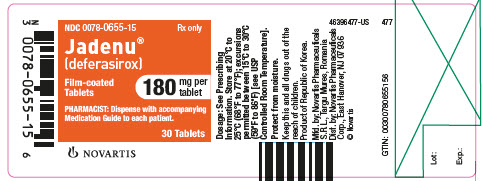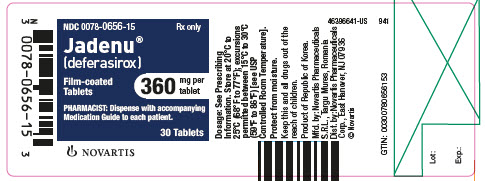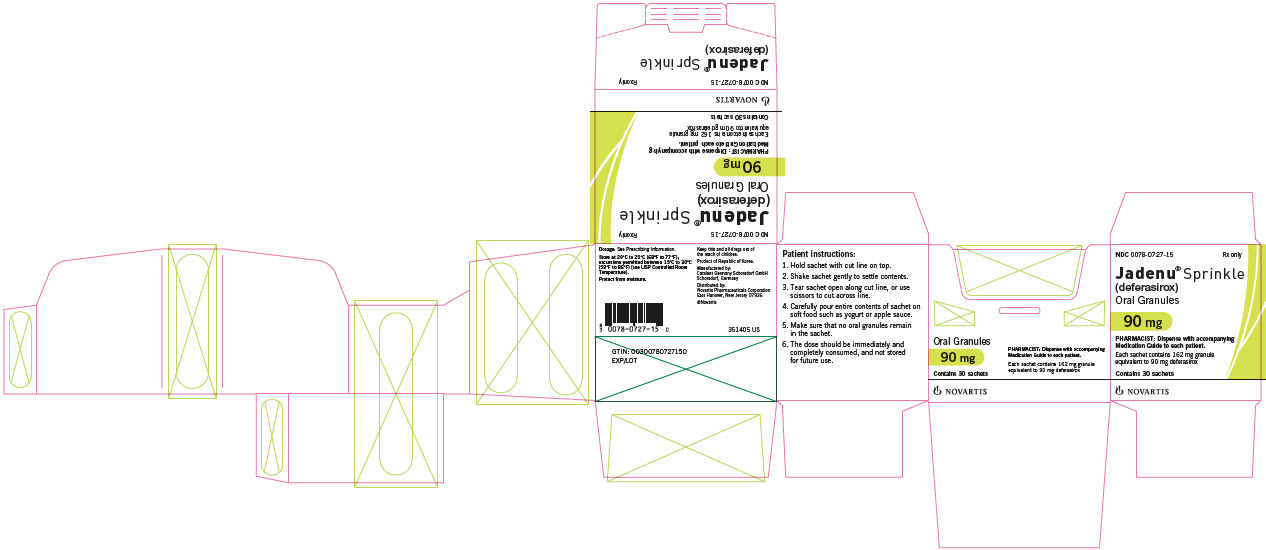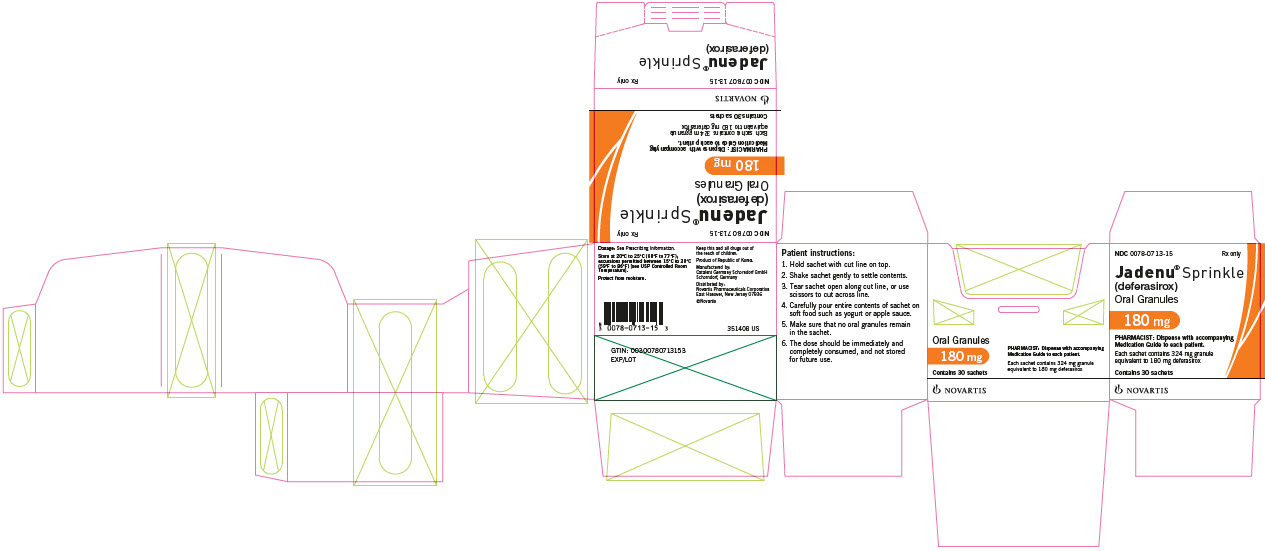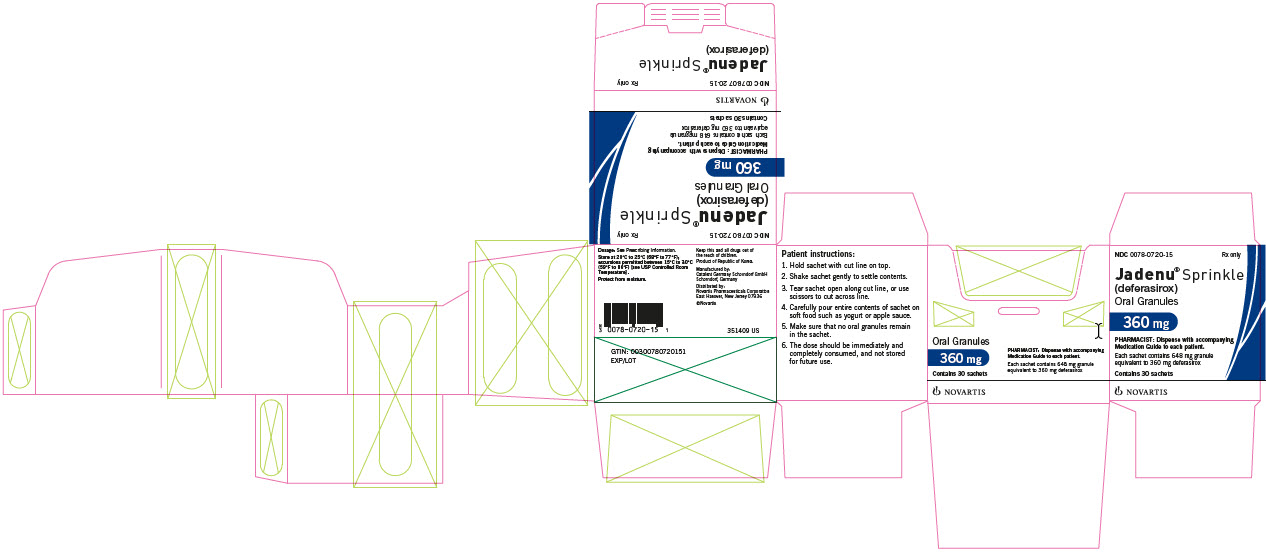 DRUG LABEL: Jadenu
NDC: 0078-0654 | Form: TABLET, FILM COATED
Manufacturer: Novartis Pharmaceuticals Corporation
Category: prescription | Type: HUMAN PRESCRIPTION DRUG LABEL
Date: 20251211

ACTIVE INGREDIENTS: DEFERASIROX 90 mg/1 1
INACTIVE INGREDIENTS: CELLULOSE, MICROCRYSTALLINE; CROSPOVIDONE; POVIDONE K30; MAGNESIUM STEARATE; SILICON DIOXIDE; POLOXAMER 188

HIGHLIGHTS OF PRESCRIBING INFORMATION

These highlights do not include all the information needed to use JADENU safely and effectively. See full prescribing information for JADENU.
JADENU® (deferasirox) tablets, for oral use
JADENU® Sprinkle (deferasirox) granules, for oral use
Initial U.S. Approval: 2005

WARNING: RENAL FAILURE, HEPATIC FAILURE, and GASTROINTESTINAL HEMORRHAGE

See full prescribing information for complete boxed warning.

JADENU may cause serious and fatal:

- acute kidney injury, including acute renal failure requiring dialysis and renal tubular toxicity including Fanconi syndrome (5.1)
- hepatic toxicity, including failure (5.2)
- gastrointestinal hemorrhage (5.3)

JADENU therapy requires close patient monitoring, including laboratory tests of renal and hepatic function. (5)

RECENT MAJOR CHANGES

Indications and Usage, Limitations of Use (1.3) | 7/2019

1 INDICATIONS AND USAGE

JADENU is an iron chelator indicated for the treatment of chronic iron overload due to blood transfusions in patients 2 years of age and older. (1.1)

JADENU is indicated for the treatment of chronic iron overload in patients 10 years of age and older with non-transfusion-dependent thalassemia (NTDT) syndromes, and with a liver iron (Fe) concentration (LIC) of at least 5 mg Fe per gram of dry weight (Fe/g dw) and a serum ferritin greater than 300 mcg/L. (1.2)

Limitations of Use:

The safety and efficacy of JADENU when administered with other iron chelation therapy have not been established. (1.3)

2 DOSAGE AND ADMINISTRATION

- Transfusional Iron Overload: Initial dose for patients with estimated glomerular filtration rate (eGFR) greater than 60 mL/min/1.73 m^2 is 14 mg per kg (calculated to nearest whole tablet or nearest whole sachet content for granules) once daily. (2.1)
- NTDT Syndromes: Initial dose for patients with eGFR greater than 60 mL/min/1.73 m^2 is 7 mg per kg (calculated to nearest whole tablet or nearest whole sachet content for granules) once daily. (2.2)
- See full prescribing information for information regarding monitoring, administration, and dose-reductions for organ impairment. (2.1, 2.2, 2.3, 2.4)

3 DOSAGE FORMS AND STRENGTHS

Tablets: 90 mg, 180 mg, 360 mg. (3)

Granules: 90 mg, 180 mg, 360 mg. (3)

4 CONTRAINDICATIONS

- Estimated GFR less than 40 mL/min/1.73 m^2. (4)
- Patients with poor performance status. (4)
- Patients with high-risk myelodysplastic syndrome (MDS). (4)
- Patients with advanced malignancies. (4)
- Patients with platelet counts less than 50 x 10^9/L. (4)
- Known hypersensitivity to deferasirox or any component of JADENU. (4)

5 WARNINGS AND PRECAUTIONS

- Acute Kidney Injury: Measure serum creatinine in duplicate before starting therapy. Monitor renal function during JADENU therapy and reduce dose or interrupt therapy for toxicity. (2.1, 2.4, 5.1)
- Hepatic Toxicity: Monitor hepatic function. Reduce dose or interrupt therapy for toxicity. (5.2)
- Fatal and Nonfatal Gastrointestinal (GI) Bleeding, Ulceration, and Irritation: Risk may be greater in patients who are taking JADENU in combination with drugs that have known ulcerogenic or hemorrhagic potential. (5.3)
- Bone Marrow Suppression: Neutropenia, agranulocytosis, worsening anemia, and thrombocytopenia, including fatal events; monitor blood counts during JADENU therapy. Interrupt therapy for toxicity. (5.4)
- Age-related Risk of Toxicity: Monitor elderly and pediatric patients closely for toxicity. (5.5)
- Hypersensitivity Reactions: Discontinue JADENU for severe reactions and institute medical intervention. (5.7)
- Severe Skin Reactions including Stevens-Johnson syndrome (SJS), toxic epidermal necrolysis (TEN), and drug reaction with eosinophilia and systemic symptoms (DRESS): Discontinue JADENU. (5.8)

6 ADVERSE REACTIONS

In patients with transfusional iron overload, the most frequently occurring (greater than 5%) adverse reactions are diarrhea, vomiting, nausea, abdominal pain, skin rashes, and increases in serum creatinine. In deferasirox-treated patients with NTDT syndromes, the most frequently occurring (greater than 5%) adverse reactions are diarrhea, rash, and nausea. (6.1)

To report SUSPECTED ADVERSE REACTIONS, contact Novartis Pharmaceuticals Corporation at 1-888-669-6682 or FDA at 1-800-FDA-1088 or www.fda.gov/medwatch.

7 DRUG INTERACTIONS

- Do not take JADENU with aluminum-containing antacid preparations. (7.1)
- Deferasirox increases the exposure of repaglinide. Consider repaglinide dose reduction and monitor blood glucose levels. (7.3)
- Avoid the use of JADENU with theophylline as theophylline levels could be increased. (7.4)
- Deferasirox increases exposure of busulfan. Monitor plasma concentrations of busulfan when coadministered with deferasirox to allow dose adjustment of busulfan, as needed. (7.7)

8 USE IN SPECIFIC POPULATIONS

Lactation: Advise women not to breastfeed. (8.2)

FULL PRESCRIBING INFORMATION

WARNING: RENAL FAILURE, HEPATIC FAILURE, and GASTROINTESTINAL HEMORRHAGE

Renal Failure

- JADENU can cause acute renal failure and death, particularly in patients with comorbidities and those who are in the advanced stages of their hematologic disorders.
- Evaluate baseline renal function prior to starting or increasing JADENU dosing in all patients. JADENU is contraindicated in adult and pediatric patients with eGFR less than 40 mL/min/1.73 m^2. Measure serum creatinine in duplicate prior to initiation of therapy. Monitor renal function at least monthly. For patients with baseline renal impairment or increased risk of acute renal failure, monitor renal function weekly for the first month, then at least monthly. Reduce the starting dose in patients with preexisting renal disease. During therapy, increase the frequency of monitoring and modify the dose for patients with an increased risk of renal impairment, including use of concomitant nephrotoxic drugs, and pediatric patients with volume depletion or overchelation [see Dosage and Administration (2.1, 2.4, 2.5), Warnings and Precautions (5.1), Adverse Reactions (6.1, 6.2)].

Hepatic Failure

- JADENU can cause hepatic injury including hepatic failure and death.
- Measure serum transaminases and bilirubin in all patients prior to initiating treatment, every 2 weeks during the first month, and at least monthly thereafter.
- Avoid use of JADENU in patients with severe (Child-Pugh C) hepatic impairment and reduce the dose in patients with moderate (Child-Pugh B) hepatic impairment [see Dosage and Administration (2.4), Warnings and Precautions (5.2)].

Gastrointestinal Hemorrhage

- JADENU can cause gastrointestinal (GI) hemorrhages, which may be fatal, especially in elderly patients who have advanced hematologic malignancies and/or low platelet counts.
- Monitor patients and discontinue JADENU for suspected GI ulceration or hemorrhage [see Warnings and Precautions (5.3)].

1 INDICATIONS AND USAGE

1.1 Treatment of Chronic Iron Overload Due to Blood Transfusions (Transfusional Iron Overload)

JADENU is indicated for the treatment of chronic iron overload due to blood transfusions (transfusional hemosiderosis) in patients 2 years of age and older.

1.2 Treatment of Chronic Iron Overload in Non-Transfusion-Dependent Thalassemia Syndromes

JADENU is indicated for the treatment of chronic iron overload in patients 10 years of age and older with non-transfusion-dependent thalassemia (NTDT) syndromes and with a liver iron concentration (LIC) of at least 5 milligrams of iron per gram of liver dry weight (mg Fe/g dw) and a serum ferritin greater than 300 mcg/L.

1.3 Limitations of Use

The safety and efficacy of JADENU when administered with other iron chelation therapy have not been established.

2 DOSAGE AND ADMINISTRATION

2.1 Transfusional Iron Overload

JADENU therapy should only be considered when a patient has evidence of chronic transfusional iron overload. The evidence should include the transfusion of at least 100 mL/kg of packed red blood cells (e.g., at least 20 units of packed red blood cells for a 40 kg person or more in individuals weighing more than 40 kg), and a serum ferritin consistently greater than 1,000 mcg/L.

Prior to starting therapy, or increasing dose, evaluate:

- Serum ferritin level
- Baseline renal function:
  - Obtain serum creatinine in duplicate (due to variations in measurements).
  - Calculate the estimated glomerular filtration rate (eGFR). Use a prediction equation appropriate for adult patients (e.g., CKD-EPI, MDRD method) and in pediatric patients (e.g., Schwartz equations).
  - Obtain urinalyses and serum electrolytes to evaluate renal tubular function [see Dosage and Administration (2.4), Warnings and Precautions (5.1)].
- Serum transaminases and bilirubin [see Dosage and Administration (2.4), Warnings and Precautions (5.2)]
- Baseline auditory and ophthalmic examinations [see Warnings and Precautions (5.10)]

Initiating Therapy:

The recommended initial dose of JADENU for patients 2 years of age and older with eGFR greater than 60 mL/min/1.73 m^2 is 14 mg per kg body weight orally, once daily. Calculate doses (mg per kg per day) to the nearest whole tablet or nearest whole sachet content for granules. Changes in weight of pediatric patients over time must be taken into account when calculating the dose.

During Therapy:

- Monitor serum ferritin monthly and adjust the dose of JADENU, if necessary, every 3 to 6 months based on serum ferritin trends.
- Use the minimum effective dose to achieve a trend of decreasing ferritin.
- Make dose adjustments in steps of 3.5 or 7 mg per kg and tailor adjustments to the individual patient’s response and therapeutic goals.
- In patients not adequately controlled with doses of 21 mg per kg (e.g., serum ferritin levels persistently above 2,500 mcg/L and not showing a decreasing trend over time), doses of up to 28 mg per kg may be considered. Doses above 28 mg per kg are not recommended [see Warnings and Precautions (5.6)].
- Adjust dose based on serum ferritin levels
  - If the serum ferritin falls below 1,000 mcg/L at 2 consecutive visits, consider dose reduction especially if the JADENU dose is greater than 17.5 mg/kg/day [see Adverse Reactions (6.1)].
  - If the serum ferritin falls below 500 mcg/L, interrupt JADENU therapy to minimize the risk of overchelation, and continue monthly monitoring [see Warnings and Precautions (5.6)].
  - Evaluate the need for ongoing chelation therapy for patients whose conditions no longer require regular blood transfusions.
  - Use the minimum effective dose to maintain iron burden in the target range [see Warnings and Precautions (5.6)].
- Monitor blood counts, liver function, renal function and ferritin monthly [see Warnings and Precautions (5.1, 5.2, 5.4)].
- Interrupt JADENU for pediatric patients who have acute illnesses, which can cause volume depletion, such as vomiting, diarrhea, or prolonged decreased oral intake, and monitor more frequently. Resume therapy as appropriate, based on assessments of renal function, when oral intake and volume status are normal [see Dosage and Administration (2.4, 2.5), Warnings and Precautions (5.1), Use in Specific Populations (8.4), Clinical Pharmacology (12.3)].

2.2 Iron Overload in Non-Transfusion-Dependent Thalassemia Syndromes

JADENU therapy should only be considered when a patient with NTDT syndrome has an LIC of at least 5 mg Fe/g dw and a serum ferritin greater than 300 mcg/L.

Prior to starting therapy, obtain:

- LIC by liver biopsy or by an FDA-cleared or approved method for identifying patients for treatment with deferasirox therapy
- Serum ferritin level on at least 2 measurements 1-month apart [see Clinical Studies (14)]
- Baseline renal function:
  - Obtain serum creatinine in duplicate (due to variations in measurements).
  - Calculate the estimated glomerular filtration rate (eGFR). Use a prediction equation appropriate for adult patients (e.g., CKD-EPI, MDRD method) and in pediatric patients (e.g., Schwartz equations).
  - Obtain urinalyses and serum electrolytes to evaluate renal tubular function [see Dosage and Administration (2.4), Warnings and Precautions (5.1)].
- Serum transaminases and bilirubin [see Dosage and Administration (2.4), Warnings and Precautions (5.2)]
- Baseline auditory and ophthalmic examinations [see Warnings and Precautions (5.10)]

Initiating Therapy:

- The recommended initial dose of JADENU for patients with eGFR greater than 60 mL/min/1.73 m^2 is 7 mg per kg body weight orally once daily. Calculate doses (mg per kg per day) to the nearest whole tablet or nearest whole sachet content for granules.
- If the baseline LIC is greater than 15 mg Fe/g dw, consider increasing the dose to 14 mg/kg/day after 4 weeks.

During Therapy:

- Monitor serum ferritin monthly to assess the patient’s response to therapy and to minimize the risk of overchelation [see Warnings and Precautions (5.6)]. Interrupt treatment when serum ferritin is less than 300 mcg/L and obtain an LIC to determine whether the LIC has fallen to less than 3 mg Fe/g dw.
- Use the minimum effective dose to achieve a trend of decreasing ferritin.
- Monitor LIC every 6 months.
- After 6 months of therapy, if the LIC remains greater than 7 mg Fe/g dw, increase the dose of deferasirox to a maximum of 14 mg/kg/day. Do not exceed a maximum of 14 mg/kg/day.
- If after 6 months of therapy, the LIC is 3 to 7 mg Fe/g dw, continue treatment with deferasirox at no more than 7 mg/kg/day.
- When the LIC is less than 3 mg Fe/g dw, interrupt treatment with deferasirox and continue to monitor the LIC.
- Monitor blood counts, liver function, renal function and ferritin monthly [see Warnings and Precautions (5.1, 5.2, 5.4)].
- Increase monitoring frequency for pediatric patients who have acute illness, which can cause volume depletion, such as vomiting, diarrhea, or prolonged decreased oral intake. Consider dose interruption until oral intake and volume status are normal [see Dosage and Administration (2.4, 2.5), Warnings and Precautions (5.1), Use in Specific Populations (8.4), Clinical Pharmacology (12.3)].

Restart treatment when the LIC rises again to more than 5 mg Fe/g dw.

2.3 Administration

Swallow JADENU tablets once daily with water or other liquids, preferably at the same time each day. Take JADENU tablets on an empty stomach or with a light meal (contains less than 7% fat content and approximately 250 calories). Examples of light meals include 1 whole wheat English muffin, 1 packet jelly (0.5 ounces), and skim milk (8 fluid ounces) or a turkey sandwich (2 oz. turkey on whole wheat bread w/ lettuce, tomato, and 1 packet mustard). Do not take JADENU tablets with aluminum-containing antacid products [see Drug Interactions (7.1)]. For patients who have difficulty swallowing whole tablets, JADENU tablets may be crushed and mixed with soft foods (e.g., yogurt or applesauce) immediately prior to use and administered orally. Commercial crushers with serrated surfaces should be avoided for crushing a single 90 mg tablet. The dose should be immediately and completely consumed and not stored for future use.

Take JADENU Sprinkle granules on an empty stomach or with a light meal [see Clinical Pharmacology (12.3)]. Administer JADENU Sprinkle granules by sprinkling the full dose on soft food (e.g., yogurt or applesauce) immediately prior to use and administered orally. JADENU Sprinkle granules should be taken once a day, preferably at the same time each day. Do not take JADENU Sprinkle granules with aluminum-containing antacid products [see Drug Interactions (7.1)].

For patients who are currently on chelation therapy with Exjade tablets for oral suspension and converting to JADENU, the dose should be about 30% lower, rounded to the nearest whole tablet or nearest whole sachet content for granules. The table below provides additional information on dosing conversion to JADENU.

 | EXJADE Tablets for oral suspension (white round tablet) | JADENU Tablets (film coated blue oval tablet) JADENU Sprinkle Granules (white to almost white granules)
Transfusion-Dependent Iron Overload
Starting Dose | 20 mg/kg/day | 14 mg/kg/day
Titration Increments | 5–10 mg/kg | 3.5–7 mg/kg
Maximum Dose | 40 mg/kg/day | 28 mg/kg/day
Non-Transfusion-Dependent Thalassemia Syndromes
Starting Dose | 10 mg/kg/day | 7 mg/kg/day
Titration Increments | 5–10 mg/kg | 3.5–7 mg/kg
Maximum Dose | 20 mg/kg/day | 14 mg/kg/day

2.4 Use in Patients With Baseline Hepatic or Renal Impairment

Patients with Baseline Hepatic Impairment

Mild (Child-Pugh A) Hepatic Impairment: No dose adjustment is necessary.

Moderate (Child-Pugh B) Hepatic Impairment: Reduce the starting dose by 50%.

Severe (Child-Pugh C) Hepatic Impairment: Avoid JADENU tablets or JADENU Sprinkle granules [see Warnings and Precautions (5.2), Use in Specific Populations (8.7)].

Patients with Baseline Renal Impairment

Do not use JADENU in adult or pediatric patients with eGFR less than 40 mL/min/1.73 m^2 [see Dosage and Administration (2.5), Contraindications (4)].

For patients with renal impairment (eGFR 40-60 mL/min/1.73 m^2), reduce the starting dose by 50% [see Use in Specific Populations (8.6)].

Exercise caution in pediatric patients with eGFR between 40 and 60 mL/minute/1.73 m^2. If treatment is needed, use the minimum effective dose and monitor renal function frequently. Individualize dose titration based on improvement in renal injury [see Use in Specific Populations (8.6)].

2.5 Dose Modifications for Decreases in Renal Function While on JADENU

JADENU is contraindicated in patients with eGFR less than 40 mL/min/1.73 m^2 [see Contraindications (4)].

For decreases in renal function while receiving JADENU [see Warnings and Precautions (5.1)], modify the dose as follows:

Transfusional Iron Overload

Adults:

- If the serum creatinine increases by 33% or more above the average baseline measurement, repeat the serum creatinine within 1 week, and if still elevated by 33% or more, reduce the dose by 7 mg per kg.

Pediatric Patients (ages 2 years–17 years):

- Reduce the dose by 7 mg per kg if eGFR decreases by greater than 33% below the average baseline measurement and repeat eGFR within 1 week.
- Interrupt JADENU for acute illnesses, which can cause volume depletion, such as vomiting, diarrhea, or prolonged decreased oral intake, and monitor more frequently. Resume therapy as appropriate, based on assessments of renal function, when oral intake and volume status are normal. Avoid use of other nephrotoxic drugs [see Warnings and Precautions (5.1)].
- In the setting of decreased renal function, evaluate the risk benefit profile of continued JADENU use. Use the minimum effective JADENU dose and monitor renal function more frequently, by evaluating tubular and glomerular function. Titrate dosing based on renal injury. Consider dose reduction or interruption and less nephrotoxic therapies until improvement of renal function. If signs of renal tubular or glomerular injury occur in the presence of other risk factors such as volume depletion, reduce or interrupt JADENU to prevent severe and irreversible renal injury [see Warnings and Precautions (5.1)].

All Patients (regardless of age):

- Discontinue therapy for eGFR less than 40 mL/min/1.73 m^2 [see Contraindications (4)].

Non-Transfusion-Dependent Thalassemia Syndromes

Adults:

- If the serum creatinine increases by 33% or more above the average baseline measurement, repeat the serum creatinine within 1 week, and if still elevated by 33% or more, interrupt therapy if the dose is 3.5 mg per kg, or reduce by 50% if the dose is 7 or 14 mg per kg.

Pediatric Patients (ages 10 years–17 years):

- Reduce the dose by 3.5 mg per kg if eGFR decreases by greater than 33% below the average baseline measurement and repeat the eGFR within 1 week.
- Increase monitoring frequency for pediatric patients who have acute illnesses, which can cause volume depletion, such as vomiting, diarrhea, or prolonged decreased oral intake. Consider dose interruption until oral intake and volume status are normal. Avoid use of other nephrotoxic drugs [see Warnings and Precautions (5.1)].
- In the setting of decreased renal function, evaluate the risk benefit profile of continued JADENU use. Use the minimum effective JADENU dose and monitor renal function more frequently, by evaluating tubular and glomerular function. Titrate dosing based on renal injury. Consider dose reduction or interruption and less nephrotoxic therapies until improvement of renal function. If signs of renal tubular or glomerular injury occur in the presence of other risk factors such as volume depletion, reduce or interrupt JADENU to prevent severe and irreversible renal injury [see Warnings and Precautions (5.1)].

All Patients (regardless of age):

- Discontinue therapy for eGFR less than 40 mL/min/1.73 m^2 [see Contraindications (4)].

2.6 Dose Modifications Based on Concomitant Medications

UDP-glucuronosyltransferases (UGT) Inducers

Concomitant use of UGT inducers decreases systemic exposure. Avoid the concomitant use of strong UGT inducers (e.g., rifampicin, phenytoin, phenobarbital, ritonavir). If you must administer JADENU tablets or JADENU Sprinkle granules with a strong UGT inducer, consider increasing the initial dose by 50%, and monitor serum ferritin levels and clinical responses for further dose modification [see Dosage and Administration (2.1, 2.2), Drug Interactions (7.5)].

Bile Acid Sequestrants

Concomitant use of bile acid sequestrants decreases systemic exposure. Avoid the concomitant use of bile acid sequestrants (e.g., cholestyramine, colesevelam, colestipol). If you must administer JADENU tablets or JADENU Sprinkle granules with a bile acid sequestrant, consider increasing the initial dose by 50%, and monitor serum ferritin levels and clinical responses for further dose modification [see Dosage and Administration (2.1, 2.2), Drug Interactions (7.6)].

3 DOSAGE FORMS AND STRENGTHS

- 90 mg JADENU tablets
  Light blue oval biconvex film-coated tablet with beveled edges, debossed with “NVR” on one side and ‘90’ on a slight upward slope in between two debossed curved lines on the other side.
- 180 mg JADENU tablets
  Medium blue oval biconvex film-coated tablet with beveled edges, debossed with “NVR” on one side and ‘180’ on a slight upward slope in between two debossed curved lines on the other side.
- 360 mg JADENU tablets
  Dark blue oval biconvex film-coated tablet with beveled edges, debossed with “NVR” on one side and ‘360’ on a slight upward slope in between two debossed curved lines on the other side.
- 90 mg JADENU Sprinkle granules
  Supplied in cartons containing 30 child resistant foil sachets. Each sachet contains 162 mg of white to almost white granules, equivalent to 90 mg deferasirox.
- 180 mg JADENU Sprinkle granules
  Supplied in cartons containing 30 child resistant foil sachets. Each sachet contains 324 mg of white to almost white granules, equivalent to 180 mg deferasirox.
- 360 mg JADENU Sprinkle granules
  Supplied in cartons containing 30 child resistant foil sachets. Each sachet contains 648 mg of white to almost white granules, equivalent to 360 mg deferasirox.

4 CONTRAINDICATIONS

JADENU is contraindicated in patients with:

- Estimated GFR less than 40 mL/min/1.73 m^2 [see Dosage and Administration (2.5), Warnings and Precautions (5.1)];
- Poor performance status [see Warnings and Precautions (5.1, 5.3)];
- High-risk myelodysplastic syndromes (this patient population was not studied and is not expected to benefit from chelation therapy);
- Advanced malignancies [see Warnings and Precautions (5.1, 5.3)];
- Platelet counts less than 50 x 10^9/L [see Warnings and Precautions (5.3, 5.4)];
- Known hypersensitivity to deferasirox or any component of JADENU [see Warnings and Precautions (5.7), Adverse Reactions (6.2)].

5 WARNINGS AND PRECAUTIONS

5.1 Acute Kidney Injury, Including Acute Renal Failure Requiring Dialysis and Renal Tubular Toxicity Including Fanconi Syndrome

JADENU is contraindicated in patients with eGFR less than 40 mL/min/1.73 m^2. Exercise caution in pediatric patients with eGFR between 40 and 60 mL/min/1.73 m^2. If treatment is needed, use the minimum effective dose and monitor renal function frequently. Individualize dose titration based on improvement in renal injury [see Use in Specific Populations (8.6)]. For patients with renal impairment (eGFR 40-60 mL/min/1.73 m^2) reduce the starting dose by 50% [see Dosage and Administration (2.4, 2.5), Use in Specific Populations (8.6)].

JADENU can cause acute kidney injury including renal failure requiring dialysis that has resulted in fatal outcomes. Based on postmarketing experience, most fatalities have occurred in patients with multiple comorbidities and who were in advanced stages of their hematological disorders. In the clinical trials, adults and pediatric deferasirox-treated patients with no preexisting renal disease experienced dose-dependent mild, non-progressive increases in serum creatinine and proteinuria. Preexisting renal disease and concomitant use of other nephrotoxic drugs may increase the risk of acute kidney injury in adult and pediatric patients. Acute illnesses associated with volume depletion and overchelation may increase the risk of acute kidney injury in pediatric patients. In pediatric patients, small decreases in eGFR can result in increases in deferasirox exposure, particularly in younger patients with body surface area typical of patients less than age 7 years. This can lead to a cycle of worsening renal function and further increases in Exjade exposure, unless the dose is reduced or interrupted. Renal tubular toxicity, including acquired Fanconi syndrome, has been reported in patients treated with deferasirox, most commonly in pediatric patients with beta-thalassemia and serum ferritin levels less than 1,500 mcg/L [see Warnings and Precautions (5.6), Adverse Reactions (6.1, 6.2), Use in Specific Populations (8.4), Clinical Pharmacology (12.3)].

Evaluate renal glomerular and tubular function before initiating therapy or increasing the dose. Use prediction equations validated for use in adult and pediatric patients to estimate GFR. Obtain serum electrolytes and urinalysis in all patients to evaluate renal tubular function [see Dosage and Administration (2.1, 2.2)].

Monitor all patients for changes in eGFR and for renal tubular toxicity weekly during the first month after initiation or modification of therapy and at least monthly thereafter. Dose reduction or interruption may be considered if abnormalities occur in levels of markers of renal tubular function and/or as clinically indicated. Monitor serum ferritin monthly to evaluate for overchelation. Use the minimum dose to establish and maintain a low iron burden. Monitor renal function more frequently in patients with preexisting renal disease or decreased renal function. In pediatric patients, interrupt JADENU during acute illnesses, which can cause volume depletion such as vomiting, diarrhea, or prolonged decreased oral intake, and monitor renal function more frequently. Promptly correct fluid deficits to prevent renal injury. Resume therapy as appropriate, based on assessments of renal function, when oral intake and volume status are normal [see Dosage and Administration (2.5), Warnings and Precautions (5.6), Adverse Reactions (6.1, 6.2), Use in Specific Populations (8.4)].

5.2 Hepatic Toxicity and Failure

JADENU can cause hepatic injury, fatal in some patients. In Study 1, 4 patients (1.3%) discontinued deferasirox because of hepatic toxicity (drug-induced hepatitis in 2 patients and increased serum transaminases in 2 additional patients). Hepatic toxicity appears to be more common in patients greater than 55 years of age. Hepatic failure was more common in patients with significant comorbidities, including liver cirrhosis and multiorgan failure [see Adverse Reactions (6.1)].

Acute liver injury and failure, including fatal outcomes, have occurred in pediatric deferasirox-treated patients. Liver failure occurred in association with acute kidney injury in pediatric patients at risk for overchelation during a volume-depleting event. Interrupt JADENU therapy when acute liver injury or acute kidney injury is suspected and during volume depletion. Monitor liver and renal function more frequently in pediatric patients who are receiving JADENU in the 14-28 mg/kg/day range and when iron burden is approaching normal. Use the minimum effective dose to achieve and maintain a low iron burden [see Dosage and Administration (2.5), Warnings and Precautions (5.6), Adverse Reactions (6.1)].

Measure transaminases [aspartate transaminase (AST) and alanine transaminase (ALT)] and bilirubin in all patients before the initiation of treatment and every 2 weeks during the first month and at least monthly thereafter. Consider dose modifications or interruption of treatment for severe or persistent elevations.

Avoid the use of JADENU in patients with severe (Child-Pugh C) hepatic impairment. Reduce the starting dose in patients with moderate (Child-Pugh B) hepatic impairment [see Dosage and Administration (2.4), Use in Specific Populations (8.7)]. Patients with mild (Child-Pugh A) or moderate (Child-Pugh B) hepatic impairment may be at higher risk for hepatic toxicity.

5.3 Gastrointestinal (GI) Ulceration, Hemorrhage, and Perforation

GI hemorrhage, including deaths, has been reported, especially in elderly patients who had advanced hematologic malignancies and/or low platelet counts. Nonfatal upper GI irritation, ulceration and hemorrhage have been reported in patients, including children and adolescents, receiving deferasirox [see Adverse Reactions (6.1)]. Monitor for signs and symptoms of GI ulceration and hemorrhage during JADENU therapy, and promptly initiate additional evaluation and treatment if a serious GI adverse reaction is suspected. The risk of GI hemorrhage may be increased when administering JADENU in combination with drugs that have ulcerogenic or hemorrhagic potential, such as nonsteroidal anti-inflammatory drugs (NSAIDs), corticosteroids, oral bisphosphonates, or anticoagulants. There have been reports of ulcers complicated with GI perforation (including fatal outcome) [see Adverse Reactions (6.2)].

5.4 Bone Marrow Suppression

Neutropenia, agranulocytosis, worsening anemia, and thrombocytopenia, including fatal events, have been reported in patients treated with deferasirox. Preexisting hematologic disorders may increase this risk. Monitor blood counts in all patients. Interrupt treatment with JADENU in patients who develop cytopenias until the cause of the cytopenia has been determined. JADENU is contraindicated in patients with platelet counts below 50 x 10^9/L.

5.5 Age-Related Risk of Toxicity

Elderly Patients

JADENU has been associated with serious and fatal adverse reactions in the postmarketing setting among adults, predominantly in elderly patients. Monitor elderly patients treated with JADENU more frequently for toxicity [see Use in Specific Populations (8.5)].

Pediatric Patients

JADENU has been associated with serious and fatal adverse reactions in pediatric patients in the postmarketing setting. These events were frequently associated with volume depletion or with continued Exjade doses in the 20-40 mg/kg/day range equivalent to 14-28 mg/kg/day JADENU when body iron burden was approaching or in the normal range. Interrupt JADENU in patients with volume depletion, and resume JADENU when renal function and fluid volume have normalized. Monitor liver and renal function more frequently during volume depletion and in patients receiving JADENU in the 14-28 mg/kg/day range when iron burden is approaching the normal range. Use the minimum effective dose to achieve and maintain a low iron burden [see Dosage and Administration (2.4), Warnings and Precautions (5.6), Use in Specific Populations (8.4)].

5.6 Overchelation

For patients with transfusional iron overload, measure serum ferritin monthly to assess the patient’s response to therapy and minimize the risk of overchelation. An analysis of pediatric patients treated with Exjade in pooled clinical trials (n = 158), found a higher rate of renal adverse reactions among patients receiving doses greater than 25 mg/kg/day equivalent to 17.5 mg/kg/day JADENU while their serum ferritin values were less than 1,000 mcg/L. Consider dose reduction or closer monitoring of renal and hepatic function, and serum ferritin levels during these periods. Use the minimum effective dose to maintain a low-iron burden [see Adverse Reactions (6.1), Use in Specific Populations (8.4)].

If the serum ferritin falls below 1,000 mcg/L at 2 consecutive visits, consider dose reduction, especially if the JADENU dose is greater than 17.5 mg/kg/day [see Adverse Reactions (6.1)]. If the serum ferritin falls below 500 mcg/L, interrupt therapy with JADENU and continue monthly monitoring. Evaluate the need for ongoing chelation for patients whose conditions do not require regular blood transfusions. Use the minimum effective dose to maintain iron burden in the target range. Continued administration of JADENU in the 14 to 28 mg/kg/day range, when the body iron burden is approaching or within the normal range can result in life-threatening adverse reactions [see Dosage and Administration (2.1)].

For patients with NTDT, measure LIC by liver biopsy or by using an FDA-cleared or approved method for monitoring patients receiving deferasirox therapy every 6 months on treatment. Interrupt JADENU administration when the LIC is less than 3 mg Fe/g dw. Measure serum ferritin monthly, and if the serum ferritin falls below 300 mcg/L, interrupt JADENU and obtain a confirmatory LIC [see Clinical Studies (14)].

5.7 Hypersensitivity

JADENU may cause serious hypersensitivity reactions (such as anaphylaxis and angioedema), with the onset of the reaction usually occurring within the first month of treatment [see Adverse Reactions (6.2)]. If reactions are severe, discontinue JADENU and institute appropriate medical intervention. JADENU is contraindicated in patients with known hypersensitivity to deferasirox products and should not be reintroduced in patients who have experienced previous hypersensitivity reactions on deferasirox products due to the risk of anaphylactic shock.

5.8 Severe Skin Reactions

Severe cutaneous adverse reactions (SCARs), including Stevens-Johnson syndrome (SJS), toxic epidermal necrolysis (TEN) and drug reaction with eosinophilia and systemic symptoms (DRESS) which could be life-threatening or fatal have been reported during deferasirox therapy [see Adverse Reactions (6.1, 6.2)]. Cases of erythema multiforme have been observed. Advise patients of the signs and symptoms of severe skin reactions, and closely monitor. If any severe skin reactions are suspected, discontinue JADENU immediately and do not reintroduce JADENU therapy.

5.9 Skin Rash

Rashes may occur during JADENU treatment [see Adverse Reactions (6.1)]. For rashes of mild to moderate severity, JADENU may be continued without dose adjustment, since the rash often resolves spontaneously. In severe cases, interrupt treatment with JADENU. Reintroduction at a lower dose with escalation may be considered after resolution of the rash.

5.10 Auditory and Ocular Abnormalities

Auditory disturbances (high frequency hearing loss, decreased hearing), and ocular disturbances (lens opacities, cataracts, elevations in intraocular pressure, and retinal disorders) were reported at a frequency of less than 1% with deferasirox therapy in the clinical studies. The frequency of auditory adverse reactions was increased among pediatric patients, who received Exjade doses greater than 25 mg/kg/day equivalent to 17.5 mg/kg/day JADENU when serum ferritin was less than 1,000 mcg/L [see Warnings and Precautions (5.6)].

Perform auditory and ophthalmic testing (including slit lamp examinations and dilated fundoscopy) before starting JADENU treatment and thereafter at regular intervals (every 12 months). If disturbances are noted, monitor more frequently. Consider dose reduction or interruption.

6 ADVERSE REACTIONS

The following clinically significant adverse reactions are also discussed in other sections of the labeling:

- Acute Kidney Injury, Including Acute Renal Failure Requiring Dialysis, and Renal Tubular Toxicity Including Fanconi Syndrome [see Warnings and Precautions (5.1, 5.6)]
- Hepatic Toxicity and Failure [see Warnings and Precautions (5.2, 5.6)]
- GI Hemorrhage [see Warnings and Precautions (5.3)]
- Bone Marrow Suppression [see Warnings and Precautions (5.4)]
- Hypersensitivity [see Warnings and Precautions (5.7)]
- Severe Skin Reactions [see Warnings and Precautions (5.8)]
- Skin Rash [see Warnings and Precautions (5.9)]
- Auditory and Ocular Abnormalities [see Warnings and Precautions (5.10)]

6.1 Clinical Trials Experience

Because clinical trials are conducted under widely varying conditions, adverse reaction rates observed in the clinical trials of a drug cannot be directly compared to rates in the clinical trials of another drug and may not reflect the rates observed in practice. JADENU was evaluated in healthy volunteer trials. Currently, there are no clinical data in patients with JADENU tablets and JADENU Sprinkle granules. JADENU contains the same active ingredient as Exjade (deferasirox) tablets for oral suspension. The following adverse reactions have been reported with Exjade tablets for oral suspension.

Transfusional Iron Overload

A total of 700 adult and pediatric patients were treated with deferasirox for 48 weeks in premarketing studies. These included 469 patients with beta-thalassemia, 99 with rare anemias, and 132 with sickle cell disease. Of these patients, 45% were male, 70% were Caucasian, and 292 patients were less than 16 years of age. In the sickle cell disease population, 89% of patients were black. Median treatment duration among the sickle cell patients was 51 weeks. Of the 700 patients treated, 469 (403 beta-thalassemia and 66 rare anemias) were entered into extensions of the original clinical protocols. In ongoing extension studies, median durations of treatment were 88 to 205 weeks.

Six hundred twenty-seven (627) patients with myelodysplastic syndrome (MDS) were enrolled across 5 uncontrolled trials. These studies varied in duration from 1 to 5 years. The discontinuation rate across studies in the first year was 46% (Adverse Events (AEs) 20%, withdrawal of consent 10%, death 8%, other 4%, lab abnormalities 3%, and lack of efficacy 1%). Among 47 patients enrolled in the study of 5-year duration, 10 remained on deferasirox at the completion of the study.

Table 1 displays adverse reactions occurring in greater than 5% of deferasirox-treated beta-thalassemia patients (Study 1), sickle cell disease patients (Study 3), and patients with MDS (MDS pool). Abdominal pain, nausea, vomiting, diarrhea, skin rashes, and increases in serum creatinine were the most frequent adverse reactions reported with a suspected relationship to deferasirox. Gastrointestinal symptoms, increases in serum creatinine, and skin rash were dose related.

Table 1. Adverse Reactionsa Occurring in > 5% of Deferasirox-treated Patients in Study 1, Study 3, and MDS Pool
 | Study 1 (Beta-thalassemia) |  | Study 3 (Sickle Cell Disease) |  | MDS Pool
Adverse Reactions | Deferasirox N = 296 n (%) | Deferoxamine N = 290 n (%) | Deferasirox N = 132 n (%) | Deferoxamine N = 63 n (%) | Deferasirox N = 627 n (%)
Abdominal Painb | 63 (21) | 41 (14) | 37 (28) | 9 (14) | 145 (23)
Diarrhea | 35 (12) | 21 (7) | 26 (20) | 3 (5) | 297 (47)
Creatinine Increasedc | 33 (11) | 0 (0) | 9 (7) | 0 | 89 (14)
Nausea | 31 (11) | 14 (5) | 30 (23) | 7 (11) | 161 (26)
Vomiting | 30 (10) | 28 (10) | 28 (21) | 10 (16) | 83 (13)
Rash | 25 (8) | 9 (3) | 14 (11) | 3 (5) | 83 (13)
Abbreviation: MDS, myelodysplastic syndrome.
aAdverse reaction frequencies are based on AEs reported regardless of relationship to study drug.
bIncludes ‘abdominal pain’, ‘abdominal pain lower’, and ‘abdominal pain upper’.
cIncludes ‘blood creatinine increased’ and ‘blood creatinine abnormal’. See also Table 2.

In Study 1, a total of 113 (38%) patients treated with deferasirox had increases in serum creatinine greater than 33% above baseline on 2 separate occasions (Table 2) and 25 (8%) patients required dose reductions. Increases in serum creatinine appeared to be dose related [see Warnings and Precautions (5.1)]. In this study, 17 (6%) patients treated with deferasirox developed elevations in serum glutamic-pyruvic transaminase (SGPT)/ALT levels greater than 5 times the upper limit of normal (ULN) at 2 consecutive visits. Of these, 2 patients had liver biopsy proven drug-induced hepatitis and both discontinued deferasirox therapy [see Warnings and Precautions (5.2)]. An additional 2 patients, who did not have elevations in SGPT/ALT greater than 5 times the ULN, discontinued deferasirox because of increased SGPT/ALT. Increases in transaminases did not appear to be dose related. Adverse reactions that led to discontinuations included abnormal liver function tests (2 patients) and drug-induced hepatitis (2 patients), skin rash, glycosuria/proteinuria, Henoch Schönlein purpura, hyperactivity/insomnia, drug fever, and cataract (1 patient each).

In Study 3, a total of 48 (36%) patients treated with deferasirox had increases in serum creatinine greater than 33% above baseline on 2 separate occasions (Table 2) [see Warnings and Precautions (5.1)]. Of the patients who experienced creatinine increases in Study 3, 8 deferasirox-treated patients required dose reductions. In this study, 5 patients in the deferasirox group developed elevations in SGPT/ALT levels greater than 5 times the ULN at 2 consecutive visits and 1 patient subsequently had deferasirox permanently discontinued. Four additional patients discontinued due to adverse reactions with a suspected relationship to study drug, including diarrhea, pancreatitis associated with gallstones, atypical tuberculosis, and skin rash.

In the MDS pool, in the first year, a total of 229 (37%) patients treated with deferasirox had increases in serum creatinine greater than 33% above baseline on 2 consecutive occasions (Table 2) and 8 (3.5%) patients permanently discontinued [see Warnings and Precautions (5.1)]. A total of 5 (0.8%) patients developed SGPT/ALT levels greater than 5 times the ULN at 2 consecutive visits. The most frequent adverse reactions that led to discontinuation included increases in serum creatinine, diarrhea, nausea, rash, and vomiting. Death was reported in the first year in 52 (8%) of patients [see Clinical Studies (14)].

Table 2. Number (%) of Patients with Increases in Serum Creatinine or SGPT/ALT in Study 1, Study 3, and MDS Pool
 | Study 1 (Beta-thalassemia) |  | Study 3 (Sickle Cell Disease) |  | MDS Pool
Laboratory Parameter | Deferasirox N = 296 n (%) | Deferoxamine N = 290 n (%) | Deferasirox N = 132 n (%) | Deferoxamine N = 63 n (%) | Deferasirox N = 627 n (%)
Serum Creatinine
Creatinine increase > 33% at 2 consecutive post-baseline visits | 113 (38) | 41 (14) | 48 (36) | 14 (22) | 229 (37)
Creatinine increase > 33% and > ULN at 2 consecutive post-baseline visits | 7 (2) | 1 (0) | 3 (2) | 2 (3) | 126 (20)
SGPT/ALT
SGPT/ALT > 5 x ULN at 2 post-baseline visits | 25 (8) | 7 (2) | 2 (2) | 0 | 9 (1)
SGPT/ALT > 5 x ULN at 2 consecutive post-baseline visits | 17 (6) | 5 (2) | 5 (4) | 0 | 5 (1)
Abbreviations: ALT, alanine transaminase; MDS, myelodysplastic syndrome; SGPT, serum glutamic-pyruvic transaminase; ULN, upper limit of normal.

Non-Transfusion-Dependent Thalassemia Syndromes

In Study 5, 110 patients with NTDT received 1 year of treatment with deferasirox 5 or 10 mg/kg/day and 56 patients received placebo in a double-blind, randomized trial. In Study 6, 130 of the patients who completed Study 5 were treated with open-label deferasirox at 5, 10, or 20 mg/kg/day (depending on the baseline LIC) for 1 year [see Clinical Studies (14)]. In Study 7, 134 patients with NTDT of 10 years of age or older with iron overload, received deferasirox tablets for oral suspension for up to 5 years, at a starting dose of 10 mg/kg/day followed by dose adjustment at Week4, and then approximately every 6 months thereafter based on LIC levels. Table 3 and 4 display the frequency of adverse reactions in patients with NTDT. Adverse reactions with a suspected relationship to study drug were included in Table 3 if they occurred at ≥ 5% of patients in Study 5.

Table 3. Adverse Reactions Occurring in Greater Than 5% Patients with NTDT
 | Study 5 |  | Study 6 | Study 7
 | Deferasirox | Placebo | Deferasirox | Deferasirox
 | N = 110 | N = 56 | N = 130 | N = 134
 | n (%) | n (%) | n (%) | n (%)
Any adverse reaction | 31 (28) | 9 (16) | 27 (21) | 50 (37)
Nausea | 7 (6) | 4 (7) | 2 (2)a | 7 (5)
Rash | 7 (6) | 1 (2) | 2 (2)a | 3 (2)a
Diarrhea | 5 (5) | 1 (2) | 7 (5) | 8 (6)
Abbreviation: NTDT, non-transfusion-dependent thalassemia.
a The occurrence of nausea, and rash are included for Study 6 and rash for Study 7 for consistency. There were no additional adverse reactions with a suspected relationship to study drug occurring in > 5% of patients in Study 6 and Study 7.

In Study 5, 1 patient in the placebo 10 mg/kg/day group experienced an ALT increase to greater than 5 times ULN and greater than 2 times baseline (Table 4). Three deferasirox-treated patients (all in the 10 mg/kg/day group) had 2 consecutive serum creatinine level increases greater than 33% from baseline and greater than ULN. Serum creatinine returned to normal in all 3 patients (in 1 spontaneously and in the other 2 after drug interruption). Two additional cases of ALT increase and 2 additional cases of serum creatinine increase were observed in the 1-year extension of Study 5. The number (%) of patients with NTDT with increase in serum creatinine or SGPT/ALT in Study 5, Study 6, and Study 7 are presented in Table 4 below.

Table 4. Number (%) of Patients with NTDT with Increases in Serum Creatinine or SGPT/ALT
 | Study 5 |  | Study 6 | Study 7
 | Deferasirox | Placebo | Deferasirox | Deferasirox
 | N = 110 | N = 56 | N = 130 | N = 134
Laboratory Parameter | n (%) | n (%) | n (%) | n (%)
Serum creatinine (> 33% increase from baseline and > ULN at ≥ 2 consecutive post-baseline values) | 3 (3) | 0 | 2 (2) | 2 (2)
SGPT/ALT (> 5 x ULN and > 2 x baseline) | 1 (1) | 1 (2) | 2 (2) | 1 (1)
Abbreviations: ALT, alanine transaminase; NTDT, non-transfusion-dependent thalassemia; SGPT, serum glutamic-pyruvic transaminase; ULN, upper limit of normal.

Proteinuria

In clinical studies, urine protein was measured monthly. Intermittent proteinuria (urine protein/creatinine ratio greater than 0.6 mg/mg) occurred in 18.6% of deferasirox-treated patients compared to 7.2% of deferoxamine-treated patients in Study 1 [see Warnings and Precautions (5.1)].

Other Adverse Reactions

In the population of more than 5,000 patients with transfusional iron overload, who have been treated with deferasirox during clinical trials, adverse reactions occurring in 0.1% to 1% of patients included gastritis, edema, sleep disorder, pigmentation disorder, dizziness, anxiety, maculopathy, cholelithiasis, pyrexia, fatigue, laryngeal pain, cataract, hearing loss, GI hemorrhage, gastric ulcer (including multiple ulcers), duodenal ulcer, renal tubular disorder (Fanconi syndrome), and acute pancreatitis (with and without underlying biliary conditions). Adverse reactions occurring in 0.01% to 0.1% of patients included optic neuritis, esophagitis, erythema multiforme, and drug reaction with eosinophilia and systemic symptoms (DRESS). Adverse reactions, which most frequently led to dose interruption or dose adjustment during clinical trials were rash, GI disorders, infections, increased serum creatinine, and increased serum transaminases.

Pooled Analysis of Pediatric Clinical Trial Data

A nested case control analysis was conducted within a deferasirox tablets for oral suspension pediatric-pooled clinical trial dataset to evaluate the effects of dose and serum ferritin level, separately and combined, on kidney function. Among 1213 children (aged 2 to 15 years) with transfusion-dependent thalassemia, 162 cases of acute kidney injury (eGFR < 90 mL/min/1.73 m^2) and 621 matched-controls with normal kidney function (eGFR > 120 mL/min/1.73 m^2) were identified. The primary findings were:

- A 26% increased risk of acute kidney injury was observed with each 5 mg/kg increase in daily Exjade dosage equivalent to 3.5 mg/kg JADENU, starting at 20 mg/kg/day equivalent to 14 mg/kg/day JADENU (95% confidence interval (CI): 1.08-1.48).

- A 25% increased risk for acute kidney injury was observed with each 250 mcg/L decrease in serum ferritin starting at 1250 mcg/L (95% CI: 1.01-1.56).

- Among pediatric patients with a serum ferritin < 1,000 mcg/L, those who received Exjade dosage > 30 mg/kg/day, equivalent to 21 mg/kg/day JADENU compared to those who received lower dosages, had a higher risk for acute kidney injury (Odds ratio (OR) = 4.47, 95% CI: 1.25-15.95), consistent with overchelation.

In addition, a cohort-based analysis of ARs was conducted in the deferasirox tablets for oral suspension pediatric pooled clinical trial data. Pediatric patients who received Exjade dose > 25 mg/kg/day equivalent to 17.5 mg/kg/day JADENU when their serum ferritin was < 1,000 mcg/L (n = 158), had a 6-fold greater rate of renal adverse reactions (Incidence Rate Ratio (IRR) = 6.00, 95% CI: 1.75-21.36), and a 2-fold greater rate of dose interruptions (IRR = 2.06, 95% CI: 1.33-3.17) compared to the time-period prior to meeting these simultaneous criteria. Adverse reactions of special interest (cytopenia, renal, hearing, and GI disorders) occurred 1.9-fold more frequently when these simultaneous criteria were met, compared to preceding time-periods (IRR = 1.91, 95% CI: 1.05-3.48) [see Warnings and Precautions (5.6)].

6.2 Postmarketing Experience

The following adverse reactions have been spontaneously reported during post-approval use of deferasirox in the transfusional iron overload setting. Because these reactions are reported voluntarily from a population of uncertain size, in which patients may have received concomitant medication, it is not always possible to reliably estimate frequency or establish a causal relationship to drug exposure.

Skin and Subcutaneous Tissue Disorders: Stevens-Johnson syndrome (SJS), leukocytoclastic vasculitis, urticaria, alopecia, toxic epidermal necrolysis (TEN)

Immune System Disorders: hypersensitivity reactions (including anaphylactic reaction and angioedema)

Renal and Urinary Disorders: acute renal failure, tubulointerstitial nephritis

Hepatobiliary Disorders: hepatic failure

GI Disorders: GI perforation

Blood and Lymphatic System Disorders: worsening anemia

5-Year Pediatric Registry

In a 5-year observational study, 267 pediatric patients 2 to < 6 years of age (at enrollment) with transfusional hemosiderosis received deferasirox. Of the 242 patients who had pre- and post-baseline eGFR measurements, 116 (48%) patients had a decrease in eGFR of ≥ 33% observed at least once. Twenty-one (18%) of these 116 patients with decreased eGFR had a dose interruption, and 15 (13%) of these 116 patients had a dose decrease within 30 days. Adverse reactions leading to permanent discontinuation from the study included liver injury (n = 11), vomiting (n = 2), renal tubular disorder (n = 1), proteinuria (n = 1), hematuria (n = 1), upper GI hemorrhage (n = 1), abdominal pain (n = 1), and hypokalemia (n = 1).

7 DRUG INTERACTIONS

7.1 Aluminum-Containing Antacid Preparations

The concomitant administration of JADENU and aluminum-containing antacid preparations has not been formally studied. Although deferasirox has a lower affinity for aluminum than for iron, do not take JADENU with aluminum-containing antacid preparations.

7.2 Agents Metabolized by CYP3A4

Deferasirox may induce CYP3A4 resulting in a decrease in CYP3A4 substrate concentration when these drugs are coadministered. Closely monitor patients for signs of reduced effectiveness when deferasirox is administered with drugs metabolized by CYP3A4 (e.g., alfentanil, aprepitant, budesonide, buspirone, conivaptan, cyclosporine, darifenacin, darunavir, dasatinib, dihydroergotamine, dronedarone, eletriptan, eplerenone, ergotamine, everolimus, felodipine, fentanyl, hormonal contraceptive agents, indinavir, fluticasone, lopinavir, lovastatin, lurasidone, maraviroc, midazolam, nisoldipine, pimozide, quetiapine, quinidine, saquinavir, sildenafil, simvastatin, sirolimus, tacrolimus, tolvaptan, tipranavir, triazolam, ticagrelor, and vardenafil) [see Clinical Pharmacology (12.3)].

7.3 Agents Metabolized by CYP2C8

Deferasirox inhibits CYP2C8 resulting in an increase in CYP2C8 substrate (e.g., repaglinide and paclitaxel) concentration when these drugs are coadministered. If JADENU and repaglinide are used concomitantly, consider decreasing the dose of repaglinide and perform careful monitoring of blood glucose levels. Closely monitor patients for signs of exposure related toxicity when JADENU is coadministered with other CYP2C8 substrates [see Clinical Pharmacology (12.3)].

7.4 Agents Metabolized by CYP1A2

Deferasirox inhibits CYP1A2 resulting in an increase in CYP1A2 substrate (e.g., alosetron, caffeine, duloxetine, melatonin, ramelteon, tacrine, theophylline, tizanidine) concentration when these drugs are coadministered. An increase in theophylline plasma concentrations could lead to clinically significant theophylline induced CNS or other adverse reactions. Avoid the concomitant use of theophylline or other CYP1A2 substrates with a narrow therapeutic index (e.g., tizanidine) with JADENU. Monitor theophylline concentrations and consider theophylline dose modification if you must coadminister theophylline with JADENU. Closely monitor patients for signs of exposure related toxicity when JADENU is coadministered with other drugs metabolized by CYP1A2 [see Clinical Pharmacology (12.3)].

7.5 Agents Inducing UDP-glucuronosyltransferase (UGT) Metabolism

Deferasirox is a substrate of UGT1A1 and to a lesser extent UGT1A3. The concomitant use of JADENU with strong UGT inducers (e.g., rifampicin, phenytoin, phenobarbital, ritonavir) may result in a decrease in JADENU efficacy due to a possible decrease in deferasirox concentration. Avoid the concomitant use of strong UGT inducers with JADENU. Consider increasing the initial dose of JADENU if you must coadminister these agents together [see Dosage and Administration (2.5), Clinical Pharmacology (12.3)].

7.6 Bile Acid Sequestrants

Avoid the concomitant use of bile acid sequestrants (e.g., cholestyramine, colesevelam, colestipol) with JADENU due to a possible decrease in deferasirox concentration. If you must coadminister these agents together, consider increasing the initial dose of JADENU [see Dosage and Administration (2.5), Clinical Pharmacology (12.3)].

7.7 Busulfan

Increased exposure of busulfan was observed with concomitant use with deferasirox. Monitor plasma concentrations of busulfan when coadministered with deferasirox to allow dose adjustment of busulfan as needed [see Clinical Pharmacology (12.3)].

8 USE IN SPECIFIC POPULATIONS

8.1 Pregnancy

Risk Summary

There are no studies with the use of JADENU in pregnant women to inform drug-associated risks.

Administration of deferasirox to rats during pregnancy resulted in decreased offspring viability and an increase in renal anomalies in male offspring at doses that were about or less than the recommended human dose on a mg/m^2 basis. No fetal effects were noted in pregnant rabbits at doses equivalent to the human recommended dose on an mg/m^2 basis. JADENU should be used during pregnancy only if the potential benefit justifies the potential risk to the fetus.

The background risk of major birth defects and miscarriage for the indicated population is unknown. All pregnancies had a background risk of birth defect, loss, or other adverse outcomes. However, the background risk in the U.S. general population of major birth defects is 2% to 4% and of miscarriage is 15% to 20% of clinically recognized pregnancies.

Data

Animal Data

In embryo-fetal developmental studies, pregnant rats and rabbits received oral deferasirox during the period of organogenesis at doses up to 100 mg/kg/day in rats and 50 mg/kg/day in rabbits (1.2 times the maximum recommended human dose (MRHD) on an mg/m^2 basis). These doses resulted in maternal toxicity but no fetal harm was observed.

In a prenatal and postnatal developmental study, pregnant rats received oral deferasirox daily from organogenesis through lactation day 20 at doses of 10, 30, and 90 mg/kg/day (0.1, 0.3, and 1.0 times the MRHD on a mg/m^2 basis). Maternal toxicity, loss of litters, and decreased offspring viability occurred at 90 mg/kg/day (1.0 times the MRHD on a mg/m^2 basis), and increases in renal anomalies in male offspring occurred at 30 mg/kg/day (0.3 times the MRHD on a mg/m^2 basis).

8.2 Lactation

Risk Summary

No data are available regarding the presence of JADENU or its metabolites in human milk, the effects of the drug on the breastfed child, or the effects of the drug on milk production. Deferasirox and its metabolites were excreted in rat milk. Because many drugs are excreted in human milk and because of the potential for serious adverse reactions in a breastfeeding child from deferasirox and its metabolites, a decision should be made whether to discontinue breastfeeding or to discontinue the drug, taking into account the importance of the drug to the mother.

8.3 Females and Males of Reproductive Potential

Contraception

Counsel patients to use non-hormonal method(s) of contraception since JADENU can render hormonal contraceptives ineffective [see Drug Interactions (7.2)].

8.4 Pediatric Use

Transfusional Iron Overload

The safety and effectiveness of JADENU have been established in pediatric patients 2 years of age and older for the treatment of transfusional iron overload [see Dosage and Administration (2.1)].

Safety and effectiveness have not been established in pediatric patients less than 2 years of age for the treatment of transfusional iron overload.

Pediatric approval for treatment of transfusional iron overload was based on clinical studies of 292 pediatric patients 2 years to less than 16 years of age with various congenital and acquired anemias. Seventy percent of these patients had beta-thalassemia [see Indications and Usage (1), Dosage and Administration (2.1), Clinical Studies (14)]. In those clinical studies, 173 children (ages 2 to < 12 years) and 119 adolescents (ages 12 to < 17 years) were exposed to deferasirox.

A trial conducted in treatment naïve pediatric patients, 2 to < 18 years of age with transfusional iron overload (NCT02435212) did not provide additional relevant information about the safety or effectiveness of the deferasirox granules dosage form (JADENU Sprinkle) compared to the deferasirox oral tablets for suspension dosage form (Exjade).

Iron Overload in Non-Transfusion-Dependent Thalassemia Syndromes

The safety and effectiveness of JADENU have been established in patients 10 years of age and older for the treatment of chronic iron overload with non-transfusion-dependent thalassemia (NTDT) syndromes [see Dosage and Administration (2.2)].

Safety and effectiveness have not been established in patients less than 10 years of age with chronic iron overload in NTDT syndromes.

Pediatric approval for treatment of NTDT syndromes with liver iron (Fe) concentration (LIC) of at least 5 mg Fe per gram of dry weight and a serum ferritin greater than 300 mcg/L was based on 16 pediatric patients treated with deferasirox therapy (10 years to less than 16 years of age) with chronic iron overload and NTDT. Use of JADENU in these age groups is supported by evidence from adequate and well-controlled studies of deferasirox in adult and pediatric patients [see Indications and Usage (1.2), Dosage and Administration (2.2), Clinical Studies (14)].

In general, risk factors for deferasirox-associated kidney injury include preexisting renal disease, volume depletion, overchelation, and concomitant use of other nephrotoxic drugs. Acute kidney injury, and acute liver injury and failure has occurred in pediatric patients. In a pooled safety analysis, pediatric patients with higher deferasirox exposures had a greater probability of renal toxicity and decreased renal function, resulting in increased deferasirox exposure and progressive renal toxicity/kidney injury. Higher rates of renal AEs have been identified among pediatric patients receiving Exjade doses greater than 25 mg/kg/day equivalent to 17.5 mg/kg/day JADENU when their serum ferritin values were less than 1,000 mcg/L [see Dosage and Administration (2.5), Warnings and Precautions (5.1, 5.6), Adverse Reactions (6.1, 6.2)].

Monitoring recommendations for all pediatric patients with Transfusional Iron Overload and NTDT

It is recommended that serum ferritin be monitored every month to assess the patient’s response to therapy and to minimize the risk of overchelation [see Warnings and Precautions (5.6)].

Monitor renal function by estimating GFR using an eGFR prediction equation appropriate for pediatric patients and evaluate renal tubular function. Monitor renal function more frequently in pediatric patients in the presence of renal toxicity risk factors, including episodes of dehydration, fever and acute illness that may result in volume depletion or decreased renal perfusion. Use the minimum effective dose [see Warnings and Precautions (5.1)].

Interrupt JADENU in pediatric patients with transfusional iron overload, and consider dose interruption in pediatric patients with non-transfusion-dependent iron overload, for acute illnesses, which can cause volume depletion, such as vomiting, diarrhea, or prolonged decreased oral intake, and monitor more frequently. Resume therapy as appropriate, based on assessments of renal function, when oral intake and volume status are normal. Evaluate the risk benefit profile of continued JADENU use in the setting of decreased renal function. Avoid use of other nephrotoxic drugs [see Dosage and Administration (2.5), Warnings and Precautions (5.1)].

Juvenile Animal Toxicity Data

Renal toxicity was observed in adult mice, rats, and marmoset monkeys administered deferasirox at therapeutic doses. In a neonatal and juvenile toxicity study in rats, deferasirox was administered orally from postpartum Day 7 through 70, which equates to a human age range of term neonate through adolescence. Increased renal toxicity was identified in juvenile rats compared to adult rats at a dose based on mg/m^2 approximately 0.4 times the recommended dose of 20 mg/kg/day. A higher frequency of renal abnormalities was noted when deferasirox was administered to non-iron overloaded animals compared to iron overloaded animals.

8.5 Geriatric Use

Four hundred thirty-one (431) patients greater than or equal to 65 years of age were studied in clinical trials of deferasirox in the transfusional iron overload setting. Two hundred twenty-five (225) of these patients were between 65 and 75 years of age while 206 were greater than or equal to 75 years of age. The majority of these patients had myelodysplastic syndrome (MDS) (n = 393). In these trials, elderly patients experienced a higher frequency of adverse reactions than younger patients. Monitor elderly patients for early signs or symptoms of adverse reactions that may require a dose adjustment. Elderly patients are at increased risk for toxicity due to the greater frequency of decreased hepatic, renal, or cardiac function, and of concomitant disease or other drug therapy. Dose selection for an elderly patient should be cautious, usually starting at the low end of the dosing range.

In elderly patients, including those with MDS, individualize the decision to remove accumulated iron based on clinical circumstances and the anticipated clinical benefit and risks of deferasirox tablets for oral suspension therapy.

8.6 Renal Impairment

JADENU is contraindicated in patients with eGFR less than 40 mL/min/1.73 m^2 [see Contraindications (4)]. For patients with renal impairment (eGFR 40 to 60 mL/min/1.73 m^2), reduce the starting dose by 50% [see Dosage and Administration (2.4), Clinical Pharmacology (12.3)]. Exercise caution in pediatric patients with an eGFR between 40 and 60 mL/min/1.73 m^2 [see Dosage and Administration (2.4)]. If treatment is needed, use the minimum effective dose with enhanced monitoring of glomerular and renal tubular function. Individualize dose titration based on improvement in renal injury [see Dosage and Administration (2.4, 2.5)].

JADENU can cause glomerular dysfunction, renal tubular toxicity, or both, and can result in acute renal failure. Monitor all patients closely for changes in eGFR and renal tubular dysfunction during JADENU treatment. If either develops, consider dose reduction, interruption or discontinuation of JADENU until glomerular or renal tubular function returns to baseline [see Dosage and Administration (2.4, 2.5), Warnings and Precautions (5.1)].

8.7 Hepatic Impairment

Avoid use in patients with severe (Child-Pugh C) hepatic impairment. For patients with moderate (Child-Pugh B) hepatic impairment, reduce the starting dose by 50%. Closely monitor patients with mild (Child-Pugh A) or moderate (Child-Pugh B) hepatic impairment for efficacy and adverse reactions that may require dose titration [see Dosage and Administration (2.4), Warnings and Precautions (5.2), Clinical Pharmacology (12.3)].

10 OVERDOSAGE

Cases of overdose (2 to 3 times the prescribed dose for several weeks) have been reported. In one case, this resulted in hepatitis which resolved without long-term consequences after a dose interruption. In one pediatric case, a dose of 2-3 times the prescribed dose for 6 days resulted in acute renal failure requiring hemofiltration and acute liver injury/failure, which were reversible with intensive care support. Single doses of deferasirox up to 80 mg per kg per day with the tablet for oral suspension formulation in iron-overloaded beta-thalassemic patients have been tolerated with nausea and diarrhea noted. In healthy subjects, single doses of up to 40 mg per kg per day with the tablet for oral suspension formulation were tolerated.

Early signs of acute overdose are digestive effects such as abdominal pain, diarrhea, nausea, and vomiting. Hepatic and renal disorders have been reported, including cases of liver enzyme and creatinine increased with recovery after treatment discontinuation. An erroneously administered single dose of 90 mg/kg led to Fanconi syndrome which resolved after treatment.

There is no specific antidote for JADENU. In case of overdose, it may be treated with induction of vomiting or gastric lavage, and by symptomatic treatment.

11 DESCRIPTION

JADENU (deferasirox) is an iron-chelating agent provided as a tablet or granules for oral use. Deferasirox is designated chemically as 4-[3,5-bis(2-hydroxyphenyl)-1H-1,2,4-triazol-1-yl]benzoic acid and has the following structural formula:

Deferasirox is a white to slightly yellow powder. It has a molecular formula C21H15N3O4 and molecular weight of 373.4 g/mol. It is insoluble in water with a pH of suspension of 4.1.

JADENU tablets contain 90 mg, 180 mg, or 360 mg deferasirox. Inactive ingredients include colloidal silicon dioxide, crospovidone, magnesium stearate, microcrystalline cellulose, poloxamer (188), and povidone (K30). The film coating contains opadry blue.

JADENU Sprinkle granules contain 90 mg, 180 mg, or 360 mg deferasirox. Inactive ingredients include colloidal silicon dioxide, crospovidone, magnesium stearate, microcrystalline cellulose, povidone (K30), poloxamer (188).

12 CLINICAL PHARMACOLOGY

12.1 Mechanism of Action

JADENU (deferasirox) is an orally active chelator that is selective for iron (as Fe^3+). It is a tridentate ligand that binds iron with high affinity in a 2:1 ratio. Although deferasirox has very low affinity for zinc and copper, there are variable decreases in the serum concentration of these trace metals after the administration of deferasirox. The clinical significance of these decreases is uncertain.

12.2 Pharmacodynamics

Pharmacodynamic effects tested in an iron balance metabolic study with the tablet for oral suspension formulation showed that deferasirox (10, 20, and 40 mg per kg per day) was able to induce a mean net iron excretion (0.119, 0.329, and 0.445 mg Fe/kg body weight per day, respectively) within the clinically relevant range (0.1 to 0.5 mg per kg per day). Iron excretion was predominantly fecal.

An analysis of pooled pediatric clinical trial data found a statistically significant relationship between exposure and the probability of renal toxicity (increase in serum creatinine and urinary protein), resulting in a decrease in renal function. Decreases in renal function resulted in an increase in deferasirox exposure which may increase the probability of renal toxicity.

Cardiac Electrophysiology

At the maximum approved recommended dose, deferasirox does not prolong the QT interval to any clinically relevant extent.

12.3 Pharmacokinetics

Absorption

Based on studies in patients with the tablet for oral suspension, deferasirox is absorbed following oral administration with median times to maximum plasma concentration (Tmax) of about 1.5 to 4 hours. In healthy subjects, JADENU showed comparable Tmax. The maximal concentrations (Cmax) and area under the curve (AUC0-24h, AUCτ) of deferasirox increase approximately linearly with dose after both single administration and under steady-state conditions. Exposure to deferasirox increased by an accumulation factor of 1.3 to 2.3 after multiple doses with the tablet for oral suspension formulation.

Tablets

The absolute bioavailability [as measured by area under the curve over time to infinity (AUCinf)] of deferasirox tablets for oral suspension is 70% compared to an intravenous dose. The bioavailability (as measured by AUCinf) of JADENU tablets was 36% greater than with deferasirox tablets for oral suspension. After strength-adjustment, the mean AUCinf of JADENU tablets (i.e., 360 mg strength) was similar to that of deferasirox tablets for oral suspension (i.e., 500 mg strength) under fasting conditions; however the mean Cmax was increased by 30%. The 30% increase in Cmax observed with JADENU tablets is not clinically meaningful.

The administration of JADENU tablets with a light meal (approximately 250 calories with fat content less than 7% of total calories) indicated that the AUCinf and Cmax were similar to that under fasting conditions. The administration of JADENU tablets with a high-fat meal (approximately 1,000 calories with fat content greater than 50% of total calories), increased AUCinf by 18% and Cmax by 29% compared to that under fasting conditions [see Dosage and Administration (2.3)].

Granules

The bioavailability (as measured by AUCinf) of JADENU Sprinkle granules was 52% greater than with deferasirox tablets for oral suspension. After strength-adjustment, the mean AUCinf of the JADENU Sprinkle granules (i.e., 4 x 90 mg strength) was similar to that of deferasirox tablets for oral suspension (i.e., 500 mg strength) under fasting conditions; however, the mean Cmax was increased by 34%. The 34% increase in Cmax observed with JADENU Sprinkle granules is not clinically meaningful.

The administration of JADENU Sprinkle granules with a soft meal (e.g., yogurt and applesauce) or with a low-fat (approximately 450 calories with fat content approximately 30% of total calories) indicated that the AUCinf and Cmax after a low-fat meal or soft foods were similar to that under fasting conditions. The administration of JADENU Sprinkle granules with a high-fat meal (approximately 1,000 calories with fat content greater than 50% of total calories) increased AUCinf by 18% with no changes in Cmax compared to that under fasting conditions [see Dosage and Administration (2.3)].

Distribution

Deferasirox is highly (~99%) protein bound almost exclusively to serum albumin. The percentage of deferasirox confined to the blood cells was 5% in humans. The volume of distribution at steady state (Vss) of deferasirox is 14.37 ± 2.69 L in adults.

Metabolism

Glucuronidation is the main metabolic pathway for deferasirox, with subsequent biliary excretion. Deconjugation of glucuronidates in the intestine and subsequent reabsorption (enterohepatic recycling) is likely to occur. Deferasirox is mainly glucuronidated by UGT1A1 and to a lesser extent UGT1A3. CYP450-catalyzed (oxidative) metabolism of deferasirox appears to be minor in humans (about 8%). Deconjugation of glucuronide metabolites in the intestine and subsequent reabsorption (enterohepatic recycling) was confirmed in a healthy subjects study in which the administration of cholestyramine 12 g twice daily (strongly binds to deferasirox and its conjugates) 4 and 10 hours after a single dose of deferasirox resulted in a 45% decrease in deferasirox exposure (AUCinf) by interfering with the enterohepatic recycling of deferasirox.

Excretion

Deferasirox and metabolites are primarily (84% of the dose) excreted in the feces. Renal excretion of deferasirox and metabolites is minimal (8% of the dose). The mean elimination half-life (t1/2) ranged from 8 to 16 hours following oral administration.

Drug Interactions

Midazolam: The concomitant administration of deferasirox tablets for oral suspension and CYP3A4 probe substrate midazolam resulted in a decrease of midazolam Cmax by 23% and AUCinf by 17%. In the clinical setting, this effect may be more pronounced, as the study was not adequately designed to conclusively assess the potential induction of CYP3A4 by deferasirox [see Drug Interactions (7.2)].

Repaglinide: The concomitant administration of deferasirox tablets for oral suspension (30 mg per kg/day for 4 days) and the CYP2C8 probe substrate repaglinide (single dose of 0.5 mg) increased repaglinide AUCinf to 2.3-fold and Cmax of 1.6-fold [see Drug Interactions (7.3)].

Theophylline: The concomitant administration of deferasirox tablets for oral suspension (repeated dose of 30 mg per kg/day) and the CYP1A2 substrate theophylline (single dose of 120 mg) resulted in an approximate doubling of the theophylline AUCinf and elimination half-life. The single dose Cmax was not affected, but an increase in theophylline Cmax is expected to occur with chronic dosing [see Drug Interactions (7.4)].

Rifampicin: The concomitant administration of deferasirox tablets for oral suspension (single dose of 30 mg per kg) and the strong uridine diphosphate glucuronosyltransferase (UGT) inducer rifampicin (600 mg per day for 9 days) decreased deferasirox AUCinf by 44% [see Drug Interactions (7.5)].

Cholestyramine: The concomitant administration of cholestyramine after a single dose of deferasirox tablets for oral suspension decreased deferasirox AUCinf by 45% [see Drug Interactions (7.6)].

Busulfan: Concomitant administration of deferasirox and busulfan resulted in an increase of busulfan exposure (AUC).

In vitro Studies:

Deferasirox inhibited human CYP2A6, CYP2D6, and CYP2C19 in vitro.

Deferasirox is not a substrate of P-glycoprotein, MRP1 or MRP2.

Pharmacokinetics in Specific Populations

Pediatric: Following oral administration of single or multiple doses, systemic exposure of adolescents and children to deferasirox was less than in adult patients. In children less than 6 years of age, systemic exposure was about 50% lower than in adults.

Sex: The apparent clearance is 17.5% lower in females compared to males.

Renal Impairment: Compared to patients with MDS and eGFR greater than 60 mL/min/1.73 m^2, patients with MDS and eGFR 40 to 60 mL/min/1.73 m^2 (n = 34) had approximately 50% higher mean deferasirox trough plasma concentrations.

Hepatic Impairment: In a single dose (20 mg/kg) study in patients with varying degrees of hepatic impairment, deferasirox exposure was increased compared to patients with normal hepatic function. The average total (free and bound) AUCinf of deferasirox increased 16% in 6 patients with mild (Child-Pugh A) hepatic impairment, and 76% in 6 patients with moderate (Child-Pugh B) hepatic impairment compared to 6 patients with normal hepatic function. The impact of severe (Child-Pugh C) hepatic impairment was assessed in only 1 patient.

13 NONCLINICAL TOXICOLOGY

13.1 Carcinogenesis, Mutagenesis, Impairment of Fertility

A 104-week oral carcinogenicity study in Wistar rats showed no evidence of carcinogenicity from deferasirox at doses up to 60 mg/kg/day (0.7 times the MRHD on an mg/m^2 basis). A 26-week oral carcinogenicity study in p53 (+/-) transgenic mice has shown no evidence of carcinogenicity from deferasirox at doses up to 200 mg/kg/day (1.2 times the MRHD on a mg/m^2 basis) in males and 300 mg/kg/day (1.7 times the MRHD on a mg/m^2 basis) in females.

Deferasirox was negative in the Ames test and chromosome aberration test with human peripheral blood lymphocytes. It was positive in 1 of 3 in vivo oral rat micronucleus tests.

Deferasirox at oral doses up to 75 mg/kg/day (0.9 times the MRHD on a mg/m^2 basis) was found to have no adverse effect on fertility and reproductive performance of male and female rats.

14 CLINICAL STUDIES

JADENU was evaluated in healthy subjects. There are no clinical data in patients with JADENU. JADENU contains the same active ingredient as Exjade (deferasirox) tablets for oral suspension. The following information is based on clinical trials conducted with Exjade tablets for oral suspension.

Transfusional Iron Overload

The primary efficacy study, Study 1 (NCT00061750), was a multicenter, open-label, randomized, active-comparator control study to compare deferasirox tablets for oral suspension and deferoxamine in patients with beta-thalassemia and transfusional hemosiderosis. Patients greater than or equal to 2 years of age were randomized in a 1:1 ratio to receive either oral deferasirox tablets for oral suspension at starting doses of 5, 10, 20, or 30 mg per kg once daily or subcutaneous deferoxamine at starting doses of 20 to 60 mg per kg for at least 5 days per week based on LIC at baseline (2 to 3, greater than 3 to 7, greater than 7 to 14, and greater than 14 mg Fe/g dry weight). Patients randomized to deferoxamine who had LIC values less than 7 mg Fe/g dry weight were permitted to continue on their prior deferoxamine dose, even though the dose may have been higher than specified in the protocol.

Patients were to have a liver biopsy at baseline and end of study (after 12 months) for LIC. The primary efficacy endpoint was defined as a reduction in LIC of greater than or equal to 3 mg Fe/g dry weight for baseline values greater than or equal to 10 mg Fe/g dry weight, reduction of baseline values between 7 and less than 10 to less than 7 mg Fe/g dry weight, or maintenance or reduction for baseline values less than 7 mg Fe/g dry weight.

A total of 586 patients were randomized and treated, 296 with deferasirox tablets for oral suspension and 290 with deferoxamine. The mean age was 17.1 years (range, 2 to 53 years); 52% were females and 88% were Caucasian. The primary efficacy population consisted of 553 patients (deferasirox tablets for oral suspension n = 276; deferoxamine n = 277) who had LIC evaluated at baseline and 12 months or discontinued due to an adverse reaction. The percentage of patients achieving the primary endpoint was 52.9% for deferasirox tablets for oral suspension and 66.4% for deferoxamine. The relative efficacy of deferasirox to deferoxamine cannot be determined from this study.

In patients who had an LIC at baseline and at end of study, the mean change in LIC was -2.4 mg Fe/g dry weight in patients treated with deferasirox tablets for oral suspension and -2.9 mg Fe/g dry weight in patients treated with deferoxamine.

Reduction of LIC and serum ferritin was observed with deferasirox tablet for oral suspension doses of 20 to 30 mg per kg per day. Deferasirox tablets for oral suspension doses below 20 mg per kg per day failed to provide consistent lowering of LIC and serum ferritin levels (Figure 1). Therefore, a starting dose of 20 mg per kg per day is recommended [see Dosage and Administration (2.1)].

Figure 1. Changes in Liver Iron Concentration and Serum Ferritin Following Deferasirox Tablets for Oral Suspension (5 to 30 mg per kg per day) in Study 1

Study 2 (NCT00061763) was an open-label, noncomparative trial of efficacy and safety of deferasirox tablets for oral suspension given for 1 year to patients with chronic anemias and transfusional hemosiderosis. Similar to Study 1, patients received 5, 10, 20, or 30 mg per kg per day of deferasirox tablets for oral suspension based on baseline LIC.

A total of 184 patients were treated in this study: 85 patients with beta-thalassemia and 99 patients with other congenital or acquired anemias (myelodysplastic syndromes, n = 47; Diamond-Blackfan syndrome, n = 30; other, n = 22). Nineteen percent (19%) of patients were less than 16 years of age and 16% were greater than or equal to 65 years of age. There was a reduction in the absolute LIC from baseline to end of study (-4.2 mg Fe/g dry weight).

Study 3 (NCT00067080) was a multicenter, open-label, randomized trial of the safety and efficacy of deferasirox tablets for oral suspension relative to deferoxamine given for 1 year in patients with sickle cell disease and transfusional hemosiderosis. Patients were randomized to deferasirox tablets for oral suspension at doses of 5, 10, 20, or 30 mg per kg per day or subcutaneous deferoxamine at doses of 20-60 mg per kg per day for 5 days per week according to baseline LIC.

A total of 195 patients were treated in this study: 132 with deferasirox tablets for oral suspension and 63 with deferoxamine. Forty-four percent (44%) of patients were less than 16 years of age and 91% were black. At end of study, the mean change in LIC (as measured by magnetic susceptometry by a superconducting quantum interference device) in the per protocol-1 (PP-1) population, which consisted of patients who had at least 1 post-baseline LIC assessment, was -1.3 mg Fe/g dry weight for patients receiving deferasirox tablets for oral suspension (n = 113) and -0.7 mg Fe/g dry weight for patients receiving deferoxamine (n = 54).

One-hundred five (105) patients with thalassemia major and cardiac iron overload were enrolled in a study assessing the change in cardiac magnetic resonance imaging (MRI) T2* value (measured in milliseconds, [ms]) before and after treatment with deferasirox. Cardiac T2* values at baseline ranged from 5 to less than 20 ms. The geometric mean of cardiac T2* in the 68 patients who completed 3 years of deferasirox tablets for oral suspension therapy increased from 11.98 ms at baseline to 17.12 ms at 3 years. Cardiac T2* values improved in patients with severe cardiac iron overload (less than 10 ms) and in those with mild to moderate cardiac iron overload (greater than or equal to 10 to less than 20 ms). The clinical significance of these observations is unknown.

Six hundred twenty-seven (627) patients with MDS were enrolled across 5 uncontrolled trials. Two hundred thirty-nine of the 627 patients were enrolled in trials that limited enrollment to patients with IPSS Low or Intermediate 1 risk MDS, and the remaining 388 patients were enrolled in trials that did not specify MDS risk stratification but required a life expectancy of greater than 1 year. Planned duration of treatment in these trials ranged from 1 year (365 patients) to 5 years (47 patients). These trials evaluated the effects of deferasirox tablets for oral suspension therapy on parameters of iron overload, including LIC (125 patients) and serum ferritin (627 patients). The percent of patients completing planned duration of treatment was 51% in the largest 1-year study, 52% in the 3-year study and 22% in the 5-year study. The major causes for treatment discontinuation were withdrawal of consent, adverse reaction, and death. Over 1 year of follow-up across these pooled studies, mean change in serum ferritin was -332.8 (± 2615.59) mcg/L (n = 593) and mean change in LIC was -5.9 (± 8.32) mg Fe/g dw (n = 68). Results of these pooled studies in 627 patients with MDS suggest a progressive decrease in serum ferritin and LIC beyond 1 year in those patients who are able to continue deferasirox tablets for oral suspension.

Study 4 (TELESTO; NCT 00940602) was a randomized, double-blind, placebo-controlled trial performed in 225 patients with MDS (Low/Int-1 risk) and transfusional iron overload of which 149 were treated with deferasirox and 76 received placebo. The observed hazard ratio of 0.64 (95% CI: 0.42, 0.96) suggests a positive impact of deferasirox on event-free survival (EFS, a composite endpoint defined as death, worsening cardiac function, hospitalization for congestive heart failure, liver function impairment, liver cirrhosis, or progression to acute myeloid leukemia; whichever occurred first).

Non-Transfusion-Dependent Thalassemia

Study 5 (NCT00873041) was a randomized, double-blind, placebo-controlled trial of treatment with deferasirox tablets for oral suspension for patients 10 years of age or older with NTDT syndromes and iron overload. Eligible patients had an LIC of at least 5 mg Fe/g dw measured by R2 MRI and a serum ferritin exceeding 300 mcg/L at screening (2 consecutive values at least 14 days apart from each other). A total of 166 patients were randomized, 55 to the deferasirox tablets for oral suspension 5 mg/kg/day dose group, 55 to the deferasirox tablets for oral suspension 10 mg/kg/day dose group, and 56 to placebo (28 to each matching placebo group). Doses could be increased after 6 months if the LIC exceeded 7 mg Fe/g dw and the LIC reduction from baseline was less than 15%. The patients enrolled included 89 males and 77 females. The underlying disease was beta-thalassemia intermedia in 95 (57%) patients, HbE beta-thalassemia in 49 (30%) patients, and alpha-thalassemia in 22 (13%) patients. There were 17 pediatric patients in the study. Caucasians comprised 57% of the study population and Asians comprised 42%. The median baseline LIC (range) for all patients was 12.1 (2.6 to 49.1) mg Fe/g dw. Follow-up was for 1 year. The primary efficacy endpoint of change in LIC from baseline to Week 52 was statistically significant in favor of both deferasirox dose groups compared with placebo (p less than or equal to 0.001) (Table 5). Furthermore, a statistically significant dose effect of deferasirox was observed in favor of the 10 mg/kg/day dose group (10 versus 5 mg/kg/day, p = 0.009). In a descriptive analysis, the target LIC (less than 5 mg Fe/g dw) was reached by 15 (27%) of 55 patients in the 10 mg/kg/day arm, 8 (15%) of 55 patients in the 5 mg/kg/day arm and 2 (4%) of 56 patients in the combined placebo groups.

Study 6 (NCT00873041) was an open-label trial of deferasirox tablets for oral suspension for the treatment of patients previously enrolled on Study 5, including cross-over to active treatment for those previously treated with placebo. The starting dose of deferasirox tablets for oral suspension in Study 6 was assigned based on the patient’s LIC at completion of Study 5, being 20 mg/kg/day for an LIC exceeding 15 mg Fe/g dw, 10 mg/kg/day for LIC 3 to 15 mg Fe/g dw, and observation if the LIC was less than 3 mg Fe/g dw. Patients could continue on 5 mg/kg/day if they had previously exhibited at least a 30% reduction in LIC. Doses could be increased to a maximum of 20 mg/kg/day after 6 months if the LIC was more than 7 mg Fe/g dw and the LIC reduction from baseline was less than 15%. The primary efficacy endpoint in Study 6 was the proportion of patients achieving an LIC less than 5 mg Fe/g dw. A total of 133 patients were enrolled. Twenty patients began Study 6 with an LIC less than 5 mg Fe/g dw. Of the 113 patients with a baseline LIC of at least 5 mg Fe/g dw in Study 6, the target LIC (less than 5 mg Fe/g dw) was reached by 39 patients (35%). The responders included 4 (10%) of 39 patients treated at 20 mg/kg/day for a baseline LIC exceeding 15 mg Fe/g dw, and 31 (51%) of 61 patients treated at 10 mg/kg/day for a baseline LIC between 5 and 15 mg Fe/g dw. The absolute change in LIC at Week 52 by starting dose is shown in Table 5 below.

Study 7 (NCT01709838) was an open-label, single-arm, multi-center, 5-year study to evaluate the efficacy and safety of deferasirox tablets for oral suspension in iron overloaded patients with NTDT of 10 years of age or older. All patients started treatment on 10 mg/kg/day deferasirox tablets for oral suspension for four weeks. At Week 4, dose escalation was based on baseline LIC. At Week 24 and every 6 months thereafter, further dose adjustments were made according to the LIC at that visit. Treatment was interrupted when LIC < 3 mg Fe/g dw or serum ferritin < 300 ng/mL and was re-started at 10 mg/kg/day when LIC ≥ 5 mg Fe/g dw and serum ferritin ≥ 300 ng/mL. Throughout the study, the maximum dose of deferasirox tablets for oral suspension given was 30 mg/kg/day.

A total of 134 patients were enrolled in the study. Eligible patients were required to have an LIC of at least 5 mg Fe/g dw measured by R2 MRI and a serum ferritin at least of 300 ng/mL at screening. The mean absolute change of LIC from Baseline to Week 52 was -6.7 mg Fe/g dw. The reduction in LIC was sustained until Week 260 (5 years) with the mean absolute change in LIC from Baseline to Week 260 of -10.6 mg Fe/g dw. In the subset of patients with Baseline LIC > 15 mg Fe/g dw (49 patients), 51.0% achieved a first LIC < 5 mg Fe/g dw (95% CI: 37.5, 64.4) with a median time of 28.6 months. In the subset of patients with target LIC of < 3 mg Fe/g dw (61 patients), 39.3% developed first LIC ≥ 5 mg Fe/g dw in the follow-up period, with a median time of 13.9 months.

Table 5. Absolute Change in LIC at Week 52 in Patients with NTDT
 | Deferasirox Tablets for Oral Suspension Starting Dosea
 | Placebo | 5 mg/kg/day | 10 mg/kg/day | 20 mg/kg/day
Study 5b
Number of Patients | n = 54 | n = 51 | n = 54 | -
Mean LIC at Baseline (mg Fe/g dw) | 16.1 | 13.4 | 14.4 | -
Mean Change (mg Fe/g dw) | +0.4 | -2.0 | -3.8 | -
(95% Confidence Interval) | (-0.6, +1.3) | (-2.9, -1.0) | (-4.8, -2.9) | -
Study 6
Number of Patients | - | n = 8 | n = 77 | n = 43
Mean LIC at Baseline (mg Fe/g dw) | - | 5.6 | 8.8 | 23.5
Mean Change (mg Fe/g dw) | - | -1.5 | -2.8 | -9.1
(95% Confidence Interval) | - | (-3.7, +0.7) | (-3.4, -2.2) | (-11.0, -7.3)
Study 7
Number of Patients | - | - | n = 127 | -
Mean LIC at Baseline (mg Fe/g dw) | - | - | 15.1 | -
Mean Change (mg Fe/g dw) | - | - | -6.7 | -
(95% Confidence Interval) | - | - | (-7.9, -5.5) | -
Abbreviation: LIC, liver iron concentration; NTDT, non-transfusion-dependent thalassemia.
aRandomized dose in Study 5 or assigned starting dose in Study 6 and Study 7.
bLeast square mean change for Study 5.

16 HOW SUPPLIED/STORAGE AND HANDLING

JADENU 90 mg tablets are light blue in color, film-coated, oval biconvex tablets with beveled edges, debossed with ‘NVR’ on one side and ‘90’ on a slight upward slope in between two debossed curved lines on the other side. They are available in bottles of 30 tablets……………………………………………(NDC 0078-0654-15)

JADENU 180 mg tablets are medium blue in color, film-coated, oval biconvex tablet with beveled edges, debossed with ‘NVR’ on one side and ‘180’ on a slight upward slope in between two debossed curved lines on the other side. They are available in bottles of 30 tablets……………………………………………(NDC 0078-0655-15)

JADENU 360 mg tablets are dark blue in color, film-coated, oval biconvex tablet with beveled edges, debossed with ‘NVR’ on one side and ‘360’ on a slight upward slope in between two debossed curved lines on the other side. They are available in bottles of 30 tablets……………………………………………(NDC 0078-0656-15)

Store JADENU tablets at 20°C - 25°C (68°F - 77°F); excursions are permitted to 15°C to 30°C (59°F to 86°F) [see USP Controlled Room Temperature]. Protect from moisture.

JADENU Sprinkle 90 mg granules are white to almost white granules in sachet. They are available in cartons of 30 sachets……………………………………………(NDC 0078-0727-15)

JADENU Sprinkle 180 mg granules are white to almost white granules in sachet. They are available in cartons of 30 sachets……………………………………………(NDC 0078-0713-15)

JADENU Sprinkle 360 mg granules are white to almost white granules in sachet. They are available in cartons of 30 sachets……………………………………………(NDC 0078-0720-15)

Store JADENU Sprinkle granules at 20°C to 25°C (68°F to 77°F); excursions are permitted between 15°C to 30°C (59°F to 86°F) [see USP Controlled Room Temperature]. Protect from moisture.

17 PATIENT COUNSELING INFORMATION

Advise the patient to read the FDA-approved patient labeling (Medication Guide).

Dosing Instructions

Advise patients to take JADENU tablets with water or other liquids. Advise patients to swallow JADENU tablets once daily with water or other liquids, preferably at the same time each day. Advise patients to take JADENU tablets on an empty stomach or with a light meal (contains less than 7% fat content and approximately 250 calories). Examples of light meals include 1 whole wheat English muffin, 1 packet jelly (0.5 ounces), and skim milk (8 fluid ounces) or a turkey sandwich (2 oz. turkey on whole wheat bread w/lettuce, tomato, and 1 packet mustard). For patients who have difficulty swallowing whole tablets, JADENU tablets may be crushed and mixed with soft foods (e.g., yogurt or applesauce) immediately prior to use and administered orally. Advise against the use of commercial crushers with serrated surfaces for crushing a single 90 mg tablet. Advise patients to immediately and completely consume the dose and not store it for future use [see Dosage and Administration (2.3)].

Advise patients to take JADENU Sprinkle granules by sprinkling the full dose on soft food (e.g., yogurt or applesauce) immediately prior to use and administered orally. Advise patients to take JADENU Sprinkle granules once a day, preferably at the same time each day. JADENU Sprinkle granules may be taken on an empty stomach or with a light meal.

Blood Testing

Advise patients that blood tests will be performed frequently to check for damage to kidneys, liver, or blood cells [see Warnings and Precautions (5.1, 5.2, 5.3, 5.4, 5.5)].

Acute Kidney Injury, Including Acute Renal Failure

Caution patients about the potential for kidney toxicity when taking JADENU tablets or JADENU Sprinkle granules. Inform patients of the signs and symptoms of kidney injury. Advise patients to contact their healthcare provider immediately if they experience any of these symptoms [see Warnings and Precautions (5.1)].

Hepatic Toxicity and Failure

Caution patients about the potential for hepatic toxicity when taking JADENU tablets or JADENU Sprinkle granules. Inform patients of the signs and symptoms of hepatic toxicity. Advise patients to contact their healthcare provider immediately if they experience any of these symptoms [see Warnings and Precautions (5.2)].

GI Ulceration and Hemorrhage

Caution patients about the potential for the development of GI ulcers or bleeding when taking JADENU in combination with drugs that have ulcerogenic or hemorrhagic potential, such as NSAIDs, corticosteroids, oral bisphosphonates, or anticoagulants. Inform patients of the signs and symptoms of GI ulcers or bleeding. Advise patients to contact their healthcare provider for symptoms of heartburn but to seek immediate medical attention for symptoms of GI hemorrhage [see Warnings and Precautions (5.3)].

Allergic Reactions

Serious allergic reactions (which include swelling of the throat) have been reported in patients taking JADENU, usually within the first month of treatment. If reactions are severe, advise patients to stop taking JADENU immediately and seek immediate medical attention [see Warnings and Precautions (5.7)].

Severe Skin Reactions

Severe skin reactions have been reported in patients taking JADENU tablets or JADENU Sprinkle granules. Inform patients of the signs and symptoms of severe skin reactions. If reactions are severe, advise patients to stop taking JADENU tablets or JADENU Sprinkle granules immediately and seek immediate medical attention [see Warnings and Precautions (5.8)].

Skin Rash

Skin rashes may occur during JADENU treatment. If the skin rash is severe, advise patients to stop taking JADENU and seek medical attention [see Warnings and Precautions (5.9)].

Pediatric Patients with Acute Illness

Instruct pediatric patients and their caregivers to contact their healthcare provider during episodes of acute illness, especially if the patient has not been drinking fluids or the patient has volume depletion due to fever, vomiting, or diarrhea [see Warnings and Precautions (5.1)].

Auditory and Ocular Testing

Because auditory and ocular disturbances have been reported with deferasirox, conduct auditory testing and ophthalmic testing before starting JADENU treatment and thereafter at regular intervals. Advise patients to contact their healthcare provider if they develop visual or auditory changes during treatment [see Warnings and Precautions (5.10)].

Drug Interactions

Caution patients not to take aluminum containing antacids and JADENU tablets or granules simultaneously [see Drug Interactions (7.1)].

Caution patients about potential loss of effectiveness of drugs metabolized by CYP3A4 (e.g., cyclosporine, simvastatin, hormonal contraceptive agents) when JADENU is administered with these drugs [see Drug Interactions (7.2)].

Caution patients about potential loss of effectiveness of JADENU when administered with drugs that are potent UGT inducers (e.g., rifampicin, phenytoin, phenobarbital, ritonavir). Based on serum ferritin levels and clinical response, consider increases in the dose of JADENU when concomitantly used with potent UGT inducers [see Drug Interactions (7.5)].

Caution patients about potential loss of effectiveness of JADENU when administered with drugs that are bile acid sequestrants (e.g., cholestyramine, colesevelam, colestipol). Based on serum ferritin levels and clinical response, consider increases in the dose of JADENU when concomitantly used with bile acid sequestrants [see Drug Interactions (7.6)].

Caution patients with diabetes to monitor their glucose levels more frequently when repaglinide is used concomitantly with JADENU [see Drug Interactions (7.3)].

Handling Instructions

Advise patients to store JADENU in a dry, room-temperature environment [see How Supplied/Storage and Handling (16)].

Driving and Using Machines

Caution patients experiencing dizziness to avoid driving or operating machinery [see Adverse Reactions (6.1)].

Distributed by:
Novartis Pharmaceuticals Corporation
East Hanover, New Jersey 07936

© Novartis

T2020-107

MEDICATION GUIDE

JADENU® (ja de neu)
(deferasirox)
tablets

JADENU® (ja de neu) Sprinkle
(deferasirox)
granules

What is the most important information I should know about JADENU and JADENU Sprinkle?
JADENU and JADENU Sprinkle can cause serious side effects, including:
Kidney problems: JADENU AND JADENU Sprinkle can cause sudden (acute) kidney problems, including kidney failure that may require treatment with dialysis, and may cause death. Deaths have happened mostly in people who also have other health problems and had a blood disorder that was in an advanced stage. Adults and children who already have kidney problems and are taking certain medicines with JADENU or JADENU Sprinkle may also have an increased risk of sudden kidney problems. Be sure to tell your healthcare provider about all the medicines you take during treatment with JADENU or JADENU Sprinkle.
Your healthcare provider should do blood and urine tests to check your or your child’s kidney function before and during treatment with JADENU or JADENU Sprinkle. Call your healthcare provider right away if:

- your child becomes sick with fever, vomiting, or diarrhea and cannot drink fluids normally during treatment with JADENU or JADENU Sprinkle. Your child may be dehydrated. Your healthcare provider may need to temporarily stop treatment with JADENU or JADENU Sprinkle and treat your child for dehydration to help prevent kidney problems. Your healthcare provider may monitor your child’s kidney function more closely.
- you notice that you or your child are passing less urine than usual during treatment with JADENU or JADENU Sprinkle.

Liver problems. JADENU AND JADENU Sprinkle can cause liver problems, including liver failure that can sometimes cause death. Liver problems with JADENU or JADENU Sprinkle may be more common in people who are over 55 years of age but can also happen in children. Liver failure has happened more often in people with cirrhosis of the liver and failure of other organs. Liver failure has also happened along with kidney problems in certain children who become dehydrated. See “Kidney problems” above.

Your healthcare provider should do blood tests to check your liver function before you start and regularly during treatment with JADENU or JADENU Sprinkle. Call your healthcare provider right away, if you develop any of the following signs and symptoms:

- drowsiness
- upper right stomach-area (abdomen) pain

- yellowing or increased yellowing of your skin or eyes
- dark urine

Bleeding, ulcers, and tears of the stomach or intestine. Severe stomach and intestine bleeding (hemorrhage) that have caused death have happened in some people treated with JADENU or JADENU Sprinkle, especially in elderly people who have advanced blood cancers or low platelet counts. Some people have also had ulcers of the stomach or intestine, sometimes with tears (perforation) that have caused death. In some people who have taken JADENU, including children and adolescents, irritation of the upper gastrointestinal tract, ulcers, and bleeding have happened, but did not cause death.

Your risk of severe bleeding (hemorrhage) may be increased if you take JADENU or JADENU Sprinkle along with other medicines that can cause ulcers or bleeding, such as:

- nonsteroidal anti-inflammatory drugs (NSAIDs)
- corticosteroids

- certain osteoporosis medicines called oral bisphosphonates
- blood thinner medicines

Before you start taking JADENU or JADENU Sprinkle, tell your healthcare provider if you are taking one of these medicines. Ask your healthcare provider if you are not sure. If you develop an ulcer of the stomach or intestine, or severe bleeding, your healthcare provider may stop JADENU or JADENU Sprinkle.

Elderly people may be at a higher risk of developing serious side effects and death due to serious side effects with JADENU or JADENU Sprinkle Your healthcare provider may need to monitor you more closely during treatment with JADENU or JADENU Sprinkle.

- Tell your healthcare provider if you get heartburn during treatment with JADENU or JADENU Sprinkle.
- Get emergency medical help right away if you vomit blood or pass black or bloody stools, or if you have severe stomach-area (abdomen) pain during treatment with JADENU or JADENU Sprinkle.

See "What are the possible side effects of JADENU or JADENU Sprinkle?" for more information about side effects.

What are JADENU and JADENU Sprinkle?
JADENU and JADENU Sprinkle are prescription medicines that are used to treat:

- people 2 years of age and older who have an increased amount of iron in their blood for a long period of time (chronic), caused by repeated blood transfusions
- certain people 10 years of age or older with thalassemia who have an increased amount of iron in their blood but who are not receiving regular blood transfusions

It is not known if JADENU or JADENU Sprinkle is safe and effective when used with other medicines to treat an increased amount of iron in the blood.

It is not known if JADENU or JADENU Sprinkle is safe and effective for treating children under 2 years of age who have an increased amount of iron in their blood for a long period of time (chronic) caused by repeated blood transfusions.

It is not known if JADENU or JADENU Sprinkle is safe and effective for treating children under 10 years of age with thalassemia who have an increased amount of iron in their blood, but who are not receiving regular blood transfusions.

Do not take JADENU or JADENU Sprinkle if you:

- have certain kidney problems
- have high-risk myelodysplastic syndrome (MDS)
- have advanced cancer
- have a low platelet count
- are allergic to deferasirox or any of the ingredients in JADENU or JADENU Sprinkle. See the end of this medication guide for a list of the ingredients in JADENU and JADENU Sprinkle.

Ask your healthcare provider if you are not sure if you have any of the medical conditions listed above.

Before taking JADENU or JADENU Sprinkle tell your healthcare provider about all of your medical conditions, including if you:

- have kidney problems
- have liver problems
- have advanced cancer. See “Do not take JADENU or JADENU Sprinkle if you?”
- have a blood disorder that may increase your risk for bleeding
- are pregnant or plan to become pregnant. It is not known if JADENU or JADENU Sprinkle can harm your unborn baby. Hormonal forms of birth control may not be as effective if used during treatment with JADENU or JADENU Sprinkle. You could become pregnant. Talk to your healthcare provider about other birth control options that you can use during this time. Tell your healthcare provider right away if you become pregnant during treatment with JADENU or JADENU Sprinkle.
- are breastfeeding or plan to breastfeed. It is not known if JADENU or JADENU SPRINKLE passes into your breast milk and can harm your baby. You and your healthcare provider should decide if you will take JADENU or JADENU SPRINKLE or breastfeed. You should not do both.

Tell your healthcare provider about all the medicines you take, including prescription medicines, over-the-counter medicines, vitamins, and herbal supplements. Some medicines may affect how JADENU or JADENU Sprinkle works, and JADENU or JADENU Sprinkle may affect how other medicines work. Also, your risk of sudden kidney problems or severe bleeding may be increased if you take JADENU or JADENU Sprinkle with certain medicines. See “What is the most important information I should know about JADENU and JADENU Sprinkle?”

- Avoid taking the following medicines during treatment with JADENU and JADENU Sprinkle:
  - antacid products (medicines used to treat heartburn) that contain aluminum
  - theophylline
  - certain medicines to lower your cholesterol, called bile acid sequestrants.

Ask your healthcare provider if you are not sure if you take one of these medicines.

Know the medicines you take. Keep a list of them to show your healthcare provider or pharmacist when you get a new medicine.

How should I take JADENU?

- Take JADENU exactly as your healthcare provider tells you.
- Do not change your dose of JADENU or stop taking unless your healthcare provider tells you to.
- JADENU comes as tablets or Sprinkle granules.
  - You may take JADENU tablets or JADENU Sprinkle granules on an empty stomach or with a light meal. Examples of a light meal include:
    - 1 whole wheat English muffin, 1 packet of jelly (0.5 ounce), and skim milk (8 fluid ounces), or
    - A turkey sandwich (2 ounces of turkey on whole wheat bread with lettuce, tomato, and 1 packet of mustard)

Taking JADENU tablets:

- Take JADENU tablets by mouth with water or other liquids 1 time every day, preferably at the same time every day.
- If you have trouble swallowing the tablets whole, you may crush JADENU tablets and mix them with soft foods such as yogurt or applesauce right before taking your dose.
- Take the dose right away. Do not save any of the JADENU and soft food mixture for later use.
- Do not use store-bought pill crushers with serrated surfaces for crushing JADENU 90 mg tablets.

Taking JADENU Sprinkle granules:

- Sprinkle the prescribed dose of granules onto soft food such as yogurt or applesauce right before taking your dose.
- Take the sprinkles and soft food by mouth.

- Do not take JADENU or JADENU Sprinkle with aluminum-containing antacid products. See “Before taking JADENU or JADENU Sprinkle”.
- Tell your healthcare provider if you or your child gain or lose any weight. Your or your child’s dose of JADENU or JADENU Sprinkle may need to be adjusted.
- If you take the diabetes medicine repaglinide during treatment with JADENU, you may need to test your blood sugar (glucose) levels more often. Follow your healthcare provider’s instructions about how often to test your blood sugar during this time.
- Your healthcare provider should do blood and urine tests before, and during treatment to check how you respond to JADENU, and to monitor you for side effects. Your healthcare provider may change your dose, or temporarily or permanently stop JADENU if you have certain side effects.
- In people who have thalassemia, your healthcare provider will check the amount of iron in your liver before and during treatment with JADENU.
- If you or your child take too much JADENU or JADENU Sprinkle, call your healthcare provider right away or go to the nearest hospital emergency room. Symptoms that can happen if you take too much JADENU include: stomach-area (abdominal) pain, diarrhea, nausea and vomiting.

What should I avoid while taking JADENU or JADENU Sprinkle?

- JADENU or JADENU Sprinkle may cause dizziness. Avoid driving or operating machinery until you know how JADENU or JADENU Sprinkle affects you. Do not drive or operate machinery if JADENU or JADENU Sprinkle makes you dizzy.

What are the possible side effects of JADENU and JADENU Sprinkle?
JADENU and JADENU Sprinkle can cause serious side effects, including:

- See "What is the most important information I should know about JADENU and JADENU Sprinkle?"
- Effects on your bone marrow. JADENU and JADENU Sprinkle can affect your bone marrow and cause you to have low white blood cell count which can be serious, decreased platelets, or worsening of your anemia, and may lead to death. Your risk for effects on your bone marrow may be increased if you already have other blood disorders. Your healthcare provider will do blood tests to monitor your blood cell counts for these problems.
- Serious allergic reactions. JADENU and JADENU Sprinkle may cause serious allergic reactions, which usually start within the first month of treatment. Get medical help right away if you develop any of the following symptoms of a serious allergic reaction including:

- difficulty in breathing or swallowing
- chest pain
- rapid heartbeat
- feeling faint

- swelling of the face, lips, mouth, tongue, or throat
- severe itching of the skin with a red rash or raised bumps
- hives

- Skin rash and severe skin reactions. Skin rashes are common with JADENU and JADENU Sprinkle. If you get a more severe rash, your healthcare provider may temporarily stop JADENU and JADENU Sprinkle.

Severe skin reactions can also happen with JADENU and JADENU Sprinkle and can be life-threatening or lead to death. Get medical help right away if you develop any one or more of the following signs and symptoms of a severe skin reaction, including:

- rash or red skin
- blisters on your lips, or around your mouth or eyes
- mouth sores

- skin peeling
- high fever or flu-like symptoms
- enlarged lymph nodes

- Hearing and vision problems. JADENU or JADENU Sprinkle can cause decreased hearing and changes in your vision including cataracts, increased pressure in your eye, and problems with your retinas. Your healthcare provider should do hearing and vision tests before you start and then regularly during treatment. Your healthcare provider may decrease your dose or stop JADENU or JADENU Sprinkle if you develop hearing or vision problems.

The most common side effects in anyone who takes JADENU or JADENU Sprinkle include: diarrhea and nausea.

Other common side effects in people with too much iron in their blood due to repeated blood transfusions include: vomiting, stomach-area (abdomen) pain, and an abnormal kidney function blood test.

These are not all the possible side effects of JADENU and JADENU Sprinkle.

Call your doctor for medical advice about side effects. You may report side effects to FDA at 1-800-FDA-1088.

How should I store JADENU or JADENU Sprinkle?

- Store JADENU or JADENU Sprinkle at room temperature between 68°F to 77°F (20°C to 25°C).
- Keep the bottle closed tightly and away from moisture.

Keep JADENU or JADENU Sprinkle and all medicines out of the reach of children.

General information about the safe and effective use of JADENU and JADENU Sprinkle

Medicines are sometimes prescribed for purposes other than those listed in a Medication Guide. Do not use JADENU or JADENU Sprinkle for a condition for which it was not prescribed. Do not give it to other people, even if they have the same symptoms you have. It may harm them. You can ask your healthcare provider or pharmacist for more information about JADENU or JADENU Sprinkle.

What are the ingredients in JADENU and JADENU Sprinkle?
JADENU:
Active ingredient: deferasirox
Inactive ingredients: microcrystalline cellulose, crospovidone, povidone, magnesium stearate, colloidal silicon dioxide, and poloxamer. The film coating contains opadry blue.
JADENU Sprinkle:
Active ingredient: deferasirox
Inactive ingredients: microcrystalline cellulose, crospovidone; povidone, magnesium stearate, colloidal silicon dioxide, and poloxamer.

Distributed by: Novartis Pharmaceuticals Corporation, East Hanover, New Jersey 07936

© Novartis

For more information, go to www.JADENU.com or call 1-888-669-6682.

This Medication Guide has been approved by the U.S. Food and Drug Administration.

Revised: July 2020

T2020-108

PRINCIPAL DISPLAY PANEL

NDC 0078-0654-15 Rx only

Jadenu®
(deferasirox)

Film-coated
Tablets

90 mg per tablet

PHARMACIST: Dispense with accompanying Medication Guide to each patient.

30 Tablets

NOVARTIS

PRINCIPAL DISPLAY PANEL

NDC 0078-0655-15 Rx only

Jadenu®
(deferasirox)

Film-coated
Tablets

180 mg per tablet

PHARMACIST: Dispense with accompanying Medication Guide to each patient.

30 Tablets

NOVARTIS

PRINCIPAL DISPLAY PANEL

NDC 0078-0656-15 Rx only

Jadenu®
(deferasirox)

Film-coated
Tablets

360 mg per tablet

PHARMACIST: Dispense with accompanying Medication Guide to each patient.

30 Tablets

NOVARTIS

PRINCIPAL DISPLAY PANEL

NDC 0078-0727-15 Rx only

Jadenu® Sprinkle
(deferasirox)

Oral Granules

90 mg

PHARMACIST: Dispense with accompanying Medication Guide to each patient.

Each sachet contains 162 mg granule equivalent to 90 mg deferasirox

Contains 30 sachets

NOVARTIS

PRINCIPAL DISPLAY PANEL

NDC 0078-0713-15 Rx only

Jadenu® Sprinkle
(deferasirox)

Oral Granules

180 mg

PHARMACIST: Dispense with accompanying Medication Guide to each patient.

Each sachet contains 324 mg granule equivalent to 180 mg deferasirox

Contains 30 sachets

NOVARTIS

PRINCIPAL DISPLAY PANEL

NDC 0078-0720-15 Rx only

Jadenu® Sprinkle
(deferasirox)

Oral Granules

360 mg

PHARMACIST: Dispense with accompanying Medication Guide to each patient.

Each sachet contains 648 mg granule equivalent to 360 mg deferasirox

Contains 30 sachets

NOVARTIS